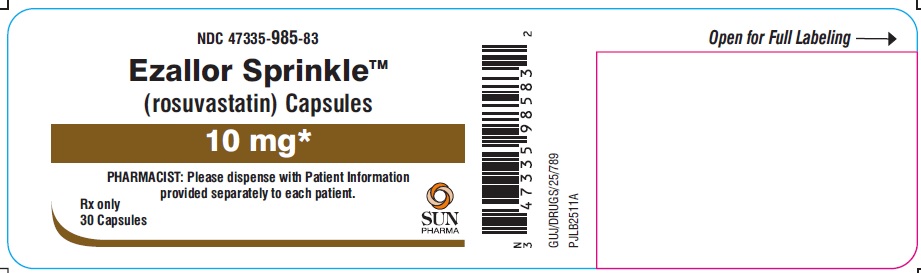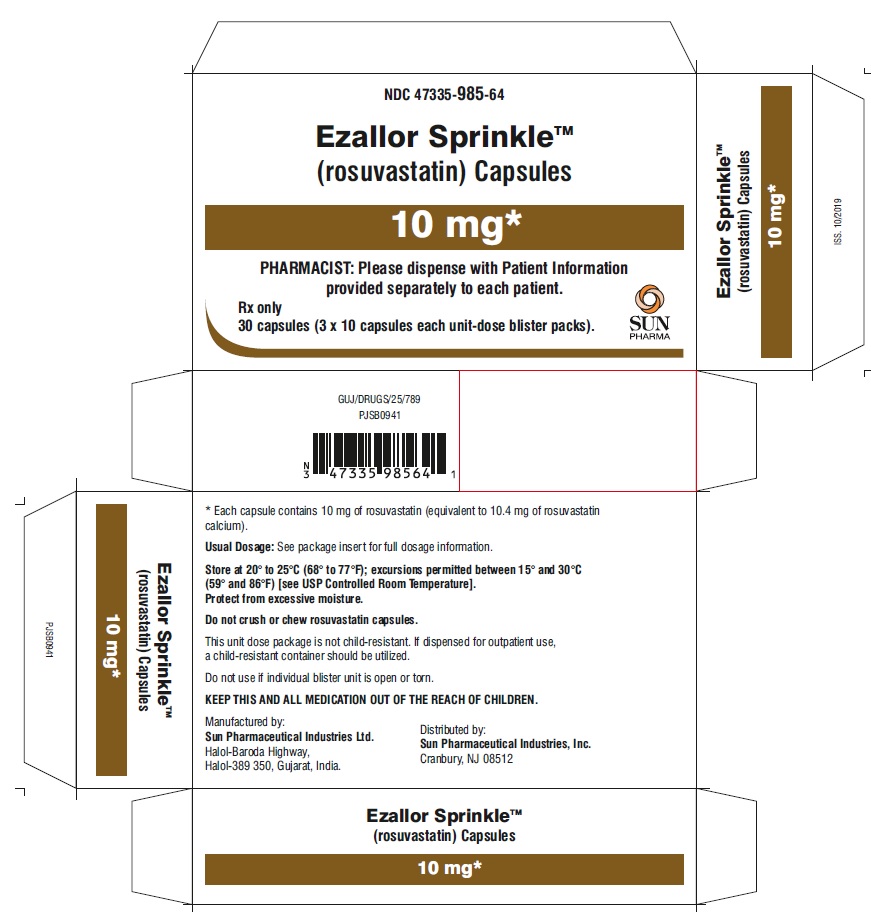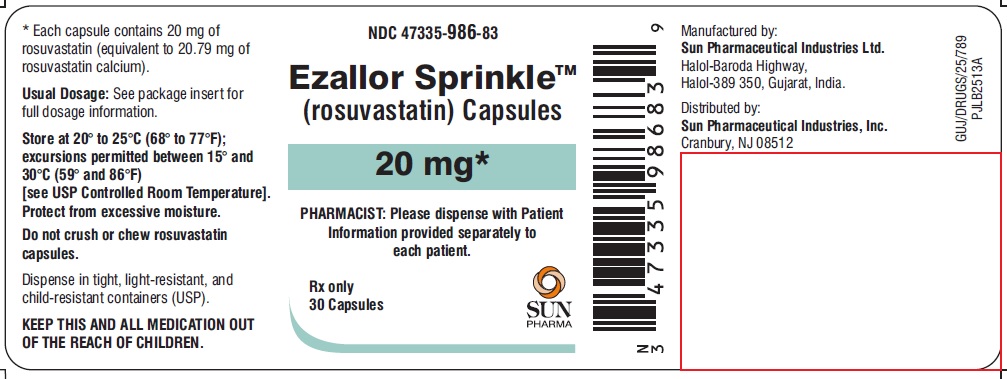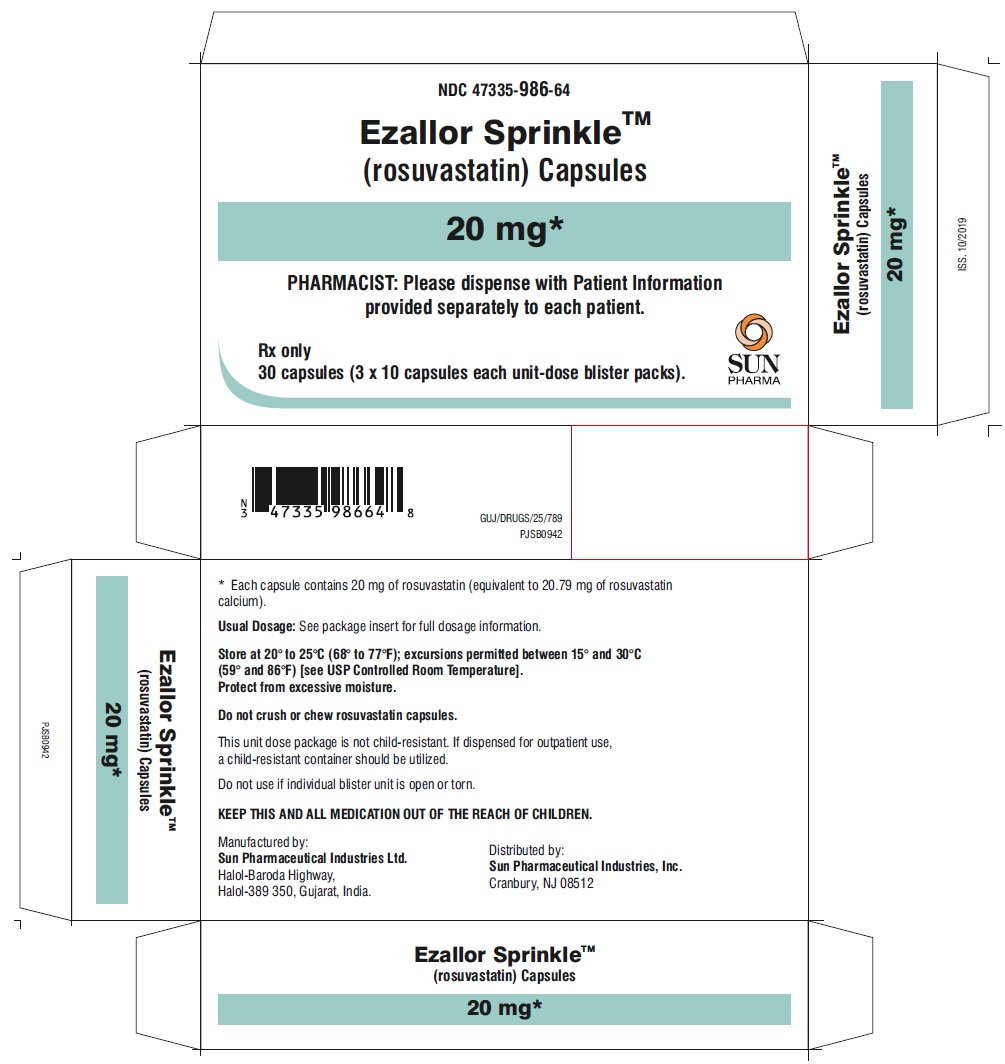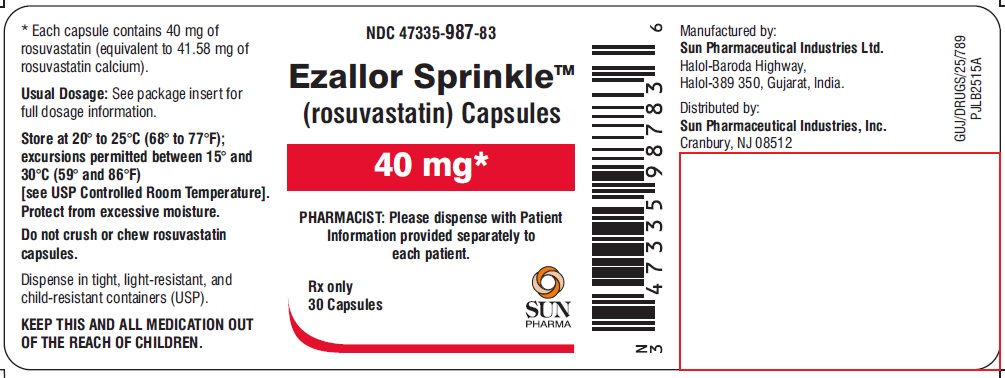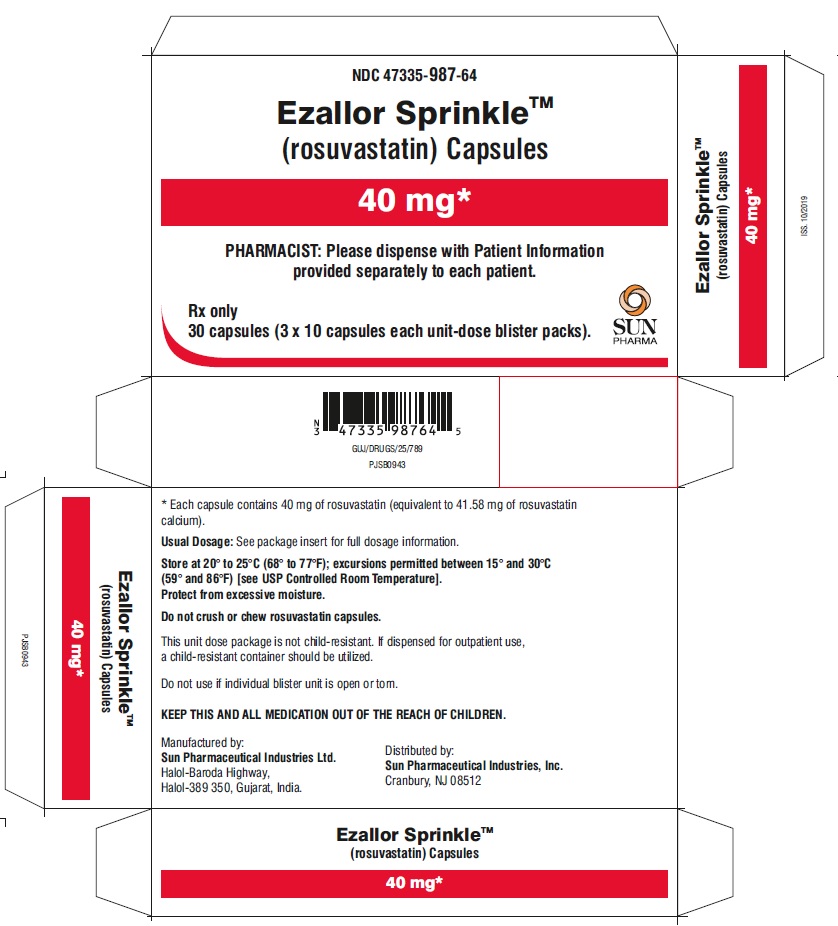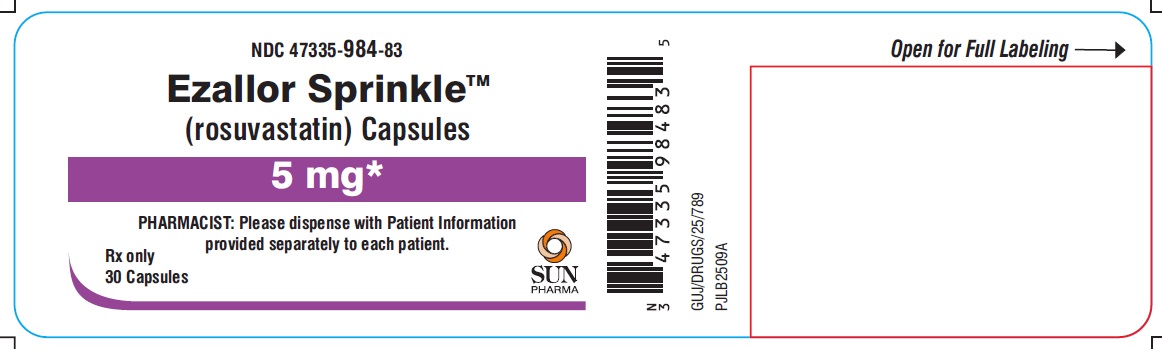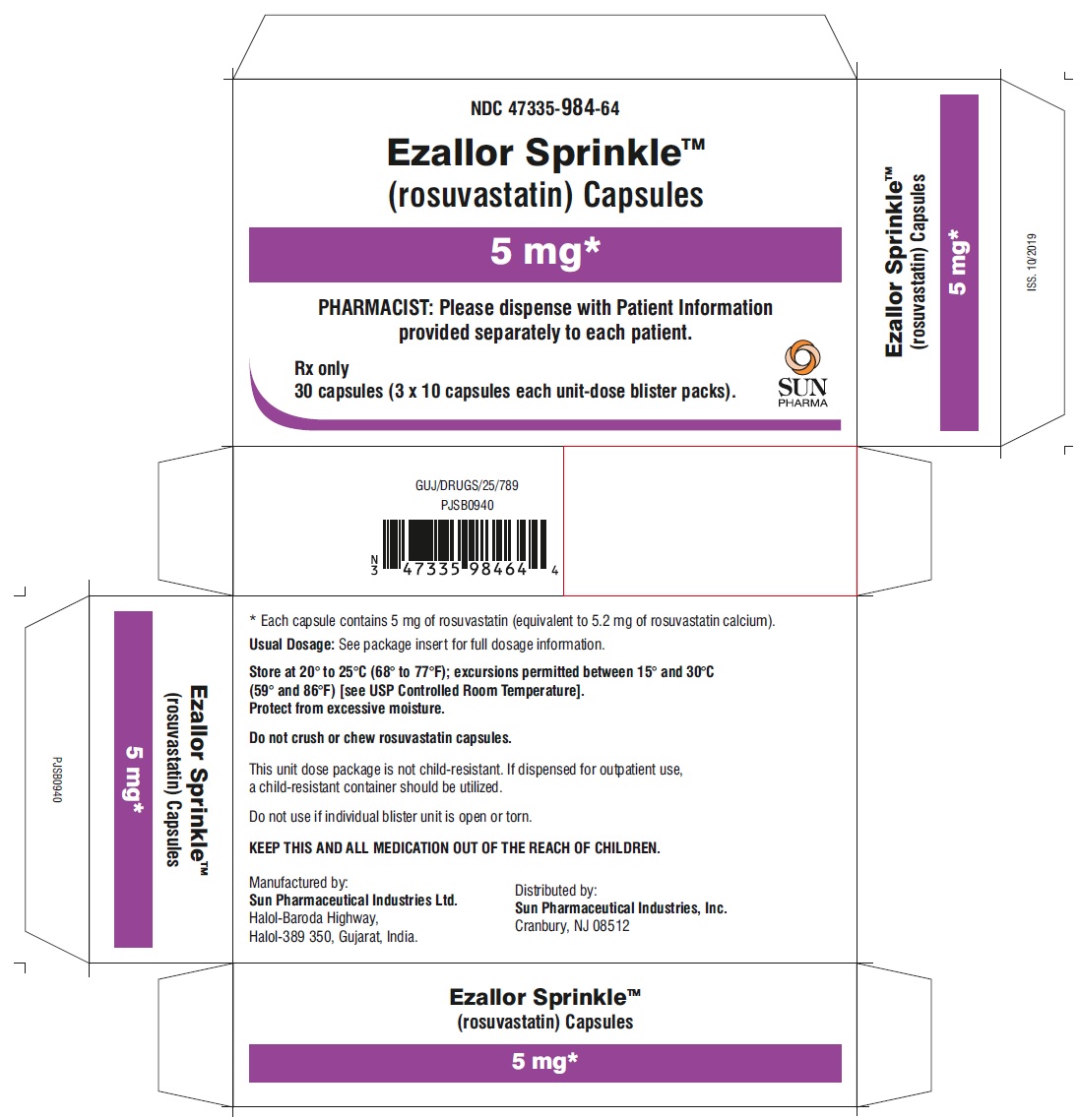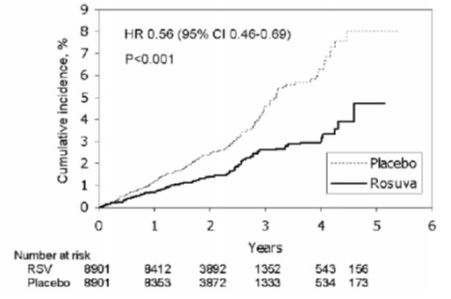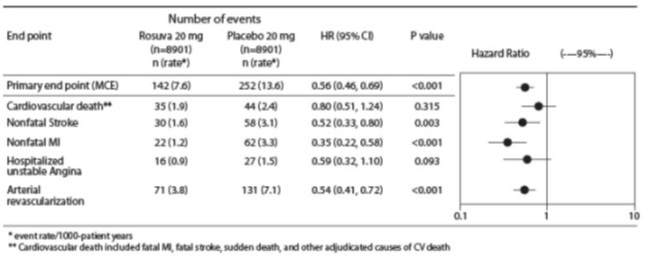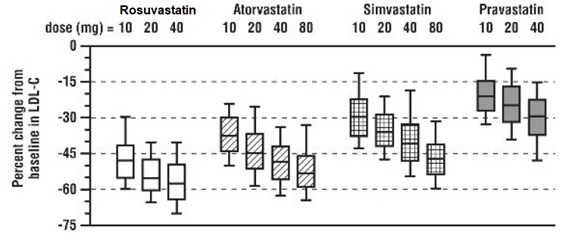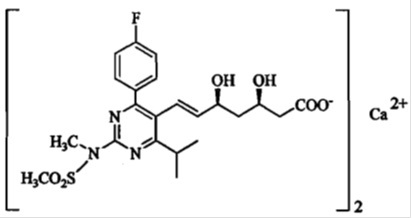 DRUG LABEL: EZALLOR SPRINKLE
NDC: 47335-984 | Form: CAPSULE
Manufacturer: Sun Pharmaceutical Industries, Inc.
Category: prescription | Type: Human Prescription Drug Label
Date: 20250311

ACTIVE INGREDIENTS: ROSUVASTATIN CALCIUM 5 mg/1 1
INACTIVE INGREDIENTS: MICROCRYSTALLINE CELLULOSE; CROSPOVIDONE; MANNITOL; MAGNESIUM OXIDE; FERRIC OXIDE YELLOW; SODIUM CITRATE, UNSPECIFIED FORM; HYPROMELLOSE, UNSPECIFIED; POLYETHYLENE GLYCOL, UNSPECIFIED; SILICON DIOXIDE; TITANIUM DIOXIDE; GELATIN, UNSPECIFIED; SODIUM LAURYL SULFATE; FD&C RED NO. 40; FD&C BLUE NO. 1; D&C RED NO. 28; SHELLAC; BUTYL ALCOHOL; PROPYLENE GLYCOL; AMMONIA; FERROSOFERRIC OXIDE; POTASSIUM HYDROXIDE

HIGHLIGHTS OF PRESCRIBING INFORMATION

These highlights do not include all the information needed to use EZALLOR SPRINKLE safely and effectively. See full prescribing information for EZALLOR SPRINKLE.
EZALLOR SPRINKLE® (rosuvastatin) capsules, for oral use
Initial U.S. Approval: 2003

RECENT MAJOR CHANGES

Indications and Usage (1) 02/2025

1 INDICATIONS AND USAGE

EZALLOR SPRINKLE is an HMG Co-A reductase inhibitor (statin) indicated: (1)

- To reduce the risk of major adverse cardiovascular (CV) events (CV death, nonfatal myocardial infarction, nonfatal stroke, or an arterial revascularization procedure) in adults without established coronary heart disease who are at increased risk of CV disease based on age, high- sensitivity C-reactive protein (hsCRP) ≥2 mg/L, and at least one additional CV risk factor.
- As an adjunct to diet to:
  - reduce LDL-C in adults with primary hyperlipidemia.
  - reduce LDL-C and slow the progression of atherosclerosis in adults.
  - reduce LDL-C in adults and pediatric patients aged 8 years and older with heterozygous familial hypercholesterolemia (HeFH).
- As an adjunct to other LDL-C-lowering therapies, or alone if such treatments are unavailable, to reduce LDL-C in adults and pediatric patients aged 7 years and older with homozygous familial hypercholesterolemia (HoFH).
- As an adjunct to diet for the treatment of adults with:

o Primary dysbetalipoproteinemia.

o Hypertriglyceridemia.

2 DOSAGE AND ADMINISTRATION

- Take orally with or without food, at any time of day. (2.1)
- Assess LDL-C when clinically appropriate, as early as 4 weeks after initiating EZALLOR SPRINKLE, and adjust dosage if necessary. (2.1)
- Adults: Recommended dosage range is 5 to 40 mg once daily. (2.1)
- Pediatric Patients with HeFH: Recommended dosage range is 5 to 10 mg once daily for patients aged 8 to less than 10 years of age, and 5 to 20 mg once daily for patients aged 10 years and older. (2.2)
- Pediatric Patients with HoFH: Recommended dosage is 20 mg once daily for patients aged 7 years and older. (2.2)
- Asian Patients: Initiate at 5 mg once daily. Consider risks and benefits of treatment if not adequately controlled at doses up to 20 mg once daily. (2.4)
- Patients with Severe Renal Impairment (not on hemodialysis): Initiate at 5 mg once daily; do not exceed 10 mg once daily. (2.5)
- See full prescribing information for EZALLOR SPRINKLE dosage and administration modifications due to drug interactions. (2.6)

3 DOSAGE FORMS AND STRENGTHS

EZALLOR SPRINKLE capsules: 5 mg, 10 mg, 20 mg, and 40 mg (3)

4 CONTRAINDICATIONS

- Acute liver failure or decompensated cirrhosis. (4)
- Hypersensitivity to rosuvastatin or any excipients in EZALLOR SPRINKLE. (4)

5 WARNINGS AND PRECAUTIONS

- Myopathy and Rhabdomyolysis: Risk factors include age 65 years or greater, uncontrolled hypothyroidism, renal impairment, concomitant use with certain other drugs, and higher EZALLOR SPRINKLE dosage. Asian patients may be at higher risk for myopathy. Discontinue EZALLOR SPRINKLE if markedly elevated CK levels occur or myopathy is diagnosed or suspected. Temporarily discontinue EZALLOR SPRINKLE in patients experiencing an acute or serious condition at high risk of developing renal failure secondary to rhabdomyolysis. Inform patients of the risk of myopathy and rhabdomyolysis when starting or increasing EZALLOR SPRINKLE dosage. Instruct patients to promptly report unexplained muscle pain, tenderness, or weakness, particularly if accompanied by malaise or fever. (5.1)
- Immune-Mediated Necrotizing Myopathy (IMNM): Rare reports of IMNM, an autoimmune myopathy, have been reported with statin use. Discontinue EZALLOR SPRINKLE if IMNM is suspected. (5.2)
- Hepatic Dysfunction: Increases in serum transaminases have occurred, some persistent. Rare reports of fatal and non-fatal hepatic failure have occurred. Consider testing liver enzymes before initiating therapy and as clinically indicated thereafter. If serious hepatic injury with clinical symptoms and/or hyperbilirubinemia or jaundice occurs, promptly discontinue EZALLOR SPRINKLE. (5.3)

6 ADVERSE REACTIONS

Most frequent adverse reactions (rate ≥ 2%) are headache, nausea, myalgia, asthenia, and constipation. (6.1)

To report SUSPECTED ADVERSE REACTIONS, contact Sun Pharmaceutical Industries, Inc. at 1-800-818-4555 or FDA at 1-800-FDA-1088 or www.fda.gov/medwatch.

7 DRUG INTERACTIONS

- See full prescribing information for details regarding concomitant use of EZALLOR SPRINKLE with other drugs that increase the risk of myopathy and rhabdomyolysis. (7.1)
- Aluminum and Magnesium Hydroxide Combination Antacids: Administer EZALLOR SPRINKLE at least 2 hours before the antacid. (7.2)
- Warfarin: Obtain INR prior to starting EZALLOR SPRINKLE. Monitor INR frequently until stable upon initiation, dose titration or discontinuation. (7.3)

8 USE IN SPECIFIC POPULATIONS

- Pregnancy: May cause fetal harm. (8.1)
- Lactation: Breastfeeding not recommended during treatment with EZALLOR SPRINKLE. (8.2)

FULL PRESCRIBING INFORMATION

1 INDICATIONS AND USAGE

EZALLOR SPRINKLE is indicated:
• To reduce the risk of major adverse cardiovascular (CV) events (CV death, nonfatal myocardial infarction, nonfatal stroke, or an arterial revascularization procedure) in adults without established coronary heart disease who are at increased risk of CV disease based on age, high-sensitivity C-reactive protein (hsCRP) ≥2 mg/L, and at least one additional CV risk factor.

• As an adjunct to diet to:
o Reduce low-density lipoprotein cholesterol (LDL-C) in adults with primary hyperlipidemia.
o Reduce LDL-C and slow the progression of atherosclerosis in adults.
o Reduce LDL-C in adults and pediatric patients aged 8 years and older with heterozygous familial hypercholesterolemia (HeFH).

• As an adjunct to other LDL-C-lowering therapies, or alone if such treatments are unavailable, to reduce LDL-C in adults and pediatric patients aged 7 years and older with homozygous familial hypercholesterolemia (HoFH).

• As an adjunct to diet for the treatment of adults with:
o Primary dysbetalipoproteinemia.
o Hypertriglyceridemia.

2 DOSAGE AND ADMINISTRATION

2.1 General Dosage and Administration Information

- Administer EZALLOR SPRINKLE orally as a single dose at any time of day, with or without food. Swallow the capsules whole. Do not crush or chew.
- Assess LDL-C when clinically appropriate, as early as 4 weeks after initiating EZALLOR SPRINKLE, and adjust the dosage if necessary.
- If a dose is missed, advise patients not to take an extra dose. Resume treatment with the next dose.
- When taking EZALLOR SPRINKLE with an aluminum and magnesium hydroxide combination antacid, administer EZALLOR SPRINKLE at least 2 hours before the antacid [see Drug Interactions (7.2)].

2.2 Recommended Dosage in Adult Patients

- The dosage range for EZALLOR SPRINKLE is 5 mg to 40 mg orally once daily.
- The recommended dose of EZALLOR SPRINKLE depends on a patient’s indication for usage, LDL-C, and individual risk for CV events.

2.3 Recommended Dosage in Pediatric Patients

Dosage in Pediatric Patients 8 Years of Age and Older with HeFH

The recommended dosage range is 5 mg to 10 mg orally once daily in patients aged 8 years to less than 10 years and 5 mg to 20 mg orally once daily in patients aged 10 years and older.

Dosage in Pediatric Patients 7 Years of Age and Older with HoFH

The recommended dosage is 20 mg orally once daily.

2.4 Recommended Dosage in Asian Patients

Initiate EZALLOR SPRINKLE at 5 mg once daily due to increased rosuvastatin plasma concentrations. Consider the risks and benefits of EZALLOR SPRINKLE when treating Asian patients not adequately controlled at doses up to 20 mg once daily [see Warnings and Precautions (5.1), Use in Specific Populations (8.8), and Clinical Pharmacology (12.3)].

2.5 Recommended Dosage in Patients with Renal Impairment

In patients with severe renal impairment (CLcr less than 30 mL/min/1.73 m^2) not on hemodialysis, the recommended starting dosage is 5 mg once daily and should not exceed 10 mg once daily [see Warnings and Precautions (5.1) and Use in Specific Populations (8.6)].

There are no dosage adjustment recommendations for patients with mild and moderate renal impairment.

2.6 Dosage Modifications Due to Drug Interactions

Table 1 displays dosage modifications for EZALLOR SPRINKLE due to drug interactions [see Warnings and Precautions (5.1) and Drug Interactions (7.1)].

Table 1: EZALLOR SPRINKLE Dosage Modifications Due to Drug Interactions

Concomitantly Used Drug | EZALLOR SPRINKLE Dosage Modifications
Cyclosporine | Do not exceed 5 mg once daily.
Teriflunomide | Do not exceed 10 mg once daily.
Enasidenib | Do not exceed 10 mg once daily.
Capmatinib | Do not exceed 10 mg once daily.
Fostamatinib | Do not exceed 20 mg once daily.
Febuxostat | Do not exceed 20 mg once daily.
Gemfibrozil | Avoid concomitant use. If used concomitantly, initiate at 5 mg once daily and do not exceed 10 mg once daily.
Tafamidis | Avoid concomitant use. If used concomitantly, initiate at 5 mg once daily and do not exceed 20 mg once daily.
Antiviral Medications
- Sofosbuvir/velpatasvir/voxilaprevir - Ledipasvir/sofosbuvir | Concomitant use not recommended.
- Simeprevir - Dasabuvir/ombitasvir/paritaprevir/ritonavir - Elbasvir/Grazoprevir - Sofosbuvir/Velpatasvir - Glecaprevir/Pibrentasvir - Atazanavir/Ritonavir - Lopinavir/Ritonavir | Initiate at 5 mg once daily. Do not exceed 10 mg once daily.
Darolutamide | Do not exceed 5 mg once daily.
Regorafenib | Do not exceed 10 mg once daily.

2.7 Preparation and Administration Instructions

EZALLOR SPRINKLE capsule should be swallowed whole. For patients unable to swallow an intact capsule, consider the following instructions based on the route of administration and refer to the accompanying Instructions for Use for complete administration instructions:

Oral Administration

- Carefully open the capsule and sprinkle the entire contents of the capsule onto at least one teaspoonful (5 mL) of room temperature applesauce or chocolate/vanilla flavored pudding.
- Stir the mixture for 10 to 15 seconds.
- Swallow the entire mixture within 60 minutes of mixing. Do not chew the mixture.
- Do not save the mixture for later use.
- Discard the unused portion immediately.

Nasogastric Tube (≥16 French) Administration

- Carefully open the capsule and empty the intact granules emptied into a 60 mL catheter tipped syringe barrel and add 40 mL of water. Do not use with liquids other than water.
- Replace the plunger and shake the syringe vigorously for 15 seconds. The granules in EZALLOR SPRINKLE capsule may start dissolving which is acceptable.
- Attach the syringe to a nasogastric tube (≥16-French) and deliver the contents of the syringe through the nasogastric tube into the stomach.
- Flush the nasogastric tube should with 20 mL of additional water after administering the mixture.
- Do not save the mixture for later use.
- Discard the unused portion immediately.

3 DOSAGE FORMS AND STRENGTHS

Hard gelatin capsules:

- 5 mg: Size “3” pink cap/off white body, imprinted axially with “984” on cap and body in black ink filled with yellow colored granules.
- 10 mg: Size “3” purple cap/off white body, imprinted axially with “985” on cap and body in black ink filled with yellow colored granules.
- 20 mg: Size “1” blue cap/off white body, imprinted axially with “986” on cap and body in black ink filled with yellow colored granules.
- 40 mg: Size “0el” green cap/white body, imprinted axially with “987” on cap and body in black ink filled with yellow colored granules.

4 CONTRAINDICATIONS

EZALLOR SPRINKLE is contraindicated in patients with:

- Acute liver failure or decompensated cirrhosis [see Warnings and Precautions (5.3)].
- Hypersensitivity to rosuvastatin or any excipients in EZALLOR SPRINKLE. Hypersensitivity reactions, including rash, pruritus, urticaria, and angioedema, have been reported with EZALLOR SPRINKLE [see Adverse Reactions (6.1)].

5 WARNINGS AND PRECAUTIONS

5.1 Myopathy and Rhabdomyolysis

EZALLOR SPRINKLE may cause myopathy [muscle pain, tenderness, or weakness associated with elevated creatine kinase (CK)] and rhabdomyolysis. Acute kidney injury secondary to myoglobinuria and rare fatalities have occurred as a result of rhabdomyolysis with statins, including EZALLOR SPRINKLE.

Risk Factors for Myopathy

Risk factors for myopathy include age 65 years or greater, uncontrolled hypothyroidism, renal impairment, concomitant use with certain other drugs (including other lipid-lowering therapies), and higher EZALLOR SPRINKLE dosage. Asian patients on EZALLOR SPRINKLE may be at higher risk for myopathy [see Drug Interactions (7.1) and Use in Specific Populations (8.8)]. The myopathy risk is greater in patients taking EZALLOR SPRINKLE 40 mg daily compared with lower EZALLOR SPRINKLE dosages.

Steps to Prevent or Reduce the Risk of Myopathy and Rhabdomyolysis

The concomitant use of EZALLOR SPRINKLE with cyclosporine or gemfibrozil is not recommended. EZALLOR SPRINKLE dosage modifications are recommended for patients taking certain antiviral medications, darolutamide, and regorafenib [see Dosage and Administration (2.6)]. Niacin, fibrates, and colchicine may also increase the risk of myopathy and rhabdomyolysis [see Drug Interactions (7.1)].

Discontinue EZALLOR SPRINKLE if markedly elevated CK levels occur or if myopathy is either diagnosed or suspected. Muscle symptoms and CK elevations may resolve if EZALLOR SPRINKLE is discontinued. Temporarily discontinue EZALLOR SPRINKLE in patients experiencing an acute or serious condition at high risk of developing renal failure secondary to rhabdomyolysis (e.g., sepsis; shock; severe hypovolemia; major surgery; trauma; severe metabolic, endocrine, or electrolyte disorders; or uncontrolled epilepsy).

Inform patients of the risk of myopathy and rhabdomyolysis when starting or increasing the EZALLOR SPRINKLE dosage. Instruct patients to promptly report any unexplained muscle pain, tenderness or weakness, particularly if accompanied by malaise or fever.

5.2 Immune-Mediated Necrotizing Myopathy

There have been rare reports of immune-mediated necrotizing myopathy (IMNM), an autoimmune myopathy, associated with statin use, including reports of recurrence when the same or a different statin was administered. IMNM is characterized by proximal muscle weakness and elevated serum creatine kinase that persist despite discontinuation of statin treatment; positive anti-HMG CoA reductase antibody; muscle biopsy showing necrotizing myopathy; and improvement with immunosuppressive agents. Additional neuromuscular and serologic testing may be necessary. Treatment with immunosuppressive agents may be required. Discontinue EZALLOR SPRINKLE if IMNM is suspected.

5.3 Hepatic Dysfunction

Increases in serum transaminases have been reported with use of EZALLOR SPRINKLE [see Adverse Reactions (6.1)]. In most cases, these changes appeared soon after initiation, were transient, were not accompanied by symptoms, and resolved or improved on continued therapy or after a brief interruption in therapy. In a pooled analysis of placebo-controlled trials, increases in serum transaminases to more than three times the ULN occurred in 1.1% of patients taking EZALLOR SPRINKLE versus 0.5% of patients treated with placebo. Marked persistent increases of hepatic transaminases have also occurred with EZALLOR Sprinkle. There have been rare postmarketing reports of fatal and non-fatal hepatic failure in patients taking statins, including EZALLOR SPRINKLE.

Patients who consume substantial quantities of alcohol and/or have a history of liver disease may be at increased risk for hepatic injury [see Use in Specific Populations (8.7)].

Consider liver enzyme testing before EZALLOR SPRINKLE initiation and when clinically indicated thereafter. EZALLOR SPRINKLE is contraindicated in patients with acute liver failure or decompensated cirrhosis [see Contraindications (4)]. If serious hepatic injury with clinical symptoms and/or hyperbilirubinemia or jaundice occurs, promptly discontinue EZALLOR SPRINKLE.

5.4 Proteinuria and Hematuria

In the rosuvastatin clinical trial program, dipstick-positive proteinuria and microscopic hematuria were observed among rosuvastatin treated patients. These findings were more frequent in patients taking rosuvastatin 40 mg, when compared to lower doses of rosuvastatin or comparator statins, though it was generally transient and was not associated with worsening renal function. Although the clinical significance of this finding is unknown, consider a dose reduction for patients on EZALLOR SPRINKLE therapy with unexplained persistent proteinuria and/or hematuria during routine urinalysis testing.

5.5 Increases in HbA1c and Fasting Serum Glucose Levels

Increases in HbA1c and fasting serum glucose levels have been reported with statins, including EZALLOR SPRINKLE. Based on clinical trial data with EZALLOR SPRINKLE, in some instances these increases may exceed the threshold for the diagnosis of diabetes mellitus [see Adverse Reactions (6.1)]. Optimize lifestyle measures, including regular exercise, maintaining a healthy body weight, and making healthy food choices.

6 ADVERSE REACTIONS

The following important adverse reactions are described below and elsewhere in the labeling:

- Myopathy and Rhabdomyolysis [see Warnings and Precautions (5.1)]
- Immune-Mediated Necrotizing Myopathy [see Warnings and Precautions (5.2)]
- Hepatic Dysfunction [see Warnings and Precautions (5.3)]
- Proteinuria and Hematuria [see Warnings and Precautions (5.4)]
- Increases in HbA1c and Fasting Serum Glucose Levels [see Warnings and Precautions (5.5)]

6.1 Clinical Trials Experience

Because clinical trials are conducted under widely varying conditions, adverse reaction rates observed in the clinical trials of a drug cannot be directly compared to rates in the clinical trials of another drug and may not reflect the rates observed in clinical practice.

Adverse reactions reported in ≥ 2% of patients in placebo-controlled clinical studies and at a rate greater than placebo are shown in Table 2. These studies had a treatment duration of up to 12 weeks.

Table 2: Adverse Reactions Reported in ≥ 2% of Patients Treated with Rosuvastatin and
> Placebo in Placebo-Controlled Trials

Adverse Reactions | Placebo N=382 % | Rosuvastatin 5 mg N=291; % | Rosuvastatin 10 mg N=283; % | Rosuvastatin 20 mg N=64; % | Rosuvastatin 40 mg N=106; % | Total Rosuvastatin 5 mg to 40 mg N=744; %
Headache | 5 | 5.5 | 4.9 | 3.1 | 8.5 | 5.5
Nausea | 3.1 | 3.8 | 3.5 | 6.3 | 0 | 3.4
Myalgia | 1.3 | 3.1 | 2.1 | 6.3 | 1.9 | 2.8
Asthenia | 2.6 | 2.4 | 3.2 | 4.7 | 0.9 | 2.7
Constipation | 2.4 | 2.1 | 2.1 | 4.7 | 2.8 | 2.4

Other adverse reactions reported in clinical studies were abdominal pain, dizziness, hypersensitivity (including rash, pruritus, urticaria, and angioedema) and pancreatitis. The following laboratory abnormalities have also been reported: dipstick-positive proteinuria and microscopic hematuria; elevated creatine phosphokinase, transaminases, glucose, glutamyl transpeptidase, alkaline phosphatase, and bilirubin; and thyroid function abnormalities.

In the METEOR study, patients were treated with rosuvastatin 40 mg (n=700) or placebo (n=281) with a mean treatment duration of 1.7 years. Adverse reactions reported in ≥2% of patients and at a rate greater than placebo are shown in Table 3.

Table 3: Adverse Reactions Reported in ≥2% of Patients Treated with Rosuvastatin and
> Placebo in the METEOR Trial

Adverse Reactions | Placebo N=281; % | Rosuvastatin 40 mg N=700; %
Myalgia | 12.1 | 12.7
Arthralgia | 7.1 | 10.1
Headache | 5.3 | 6.4
Dizziness | 2.8 | 4
Increased CPK | 0.7 | 2.6
Abdominal pain | 1.8 | 2.4
ALT greater than 3x ULN^1 | 0.7 | 2.2

^1Frequency recorded as abnormal laboratory value.

In the JUPITER study, patients were treated with rosuvastatin 20 mg (n=8,901) or placebo (n=8,901) for a mean duration of 2 years. In JUPITER, there was a significantly higher frequency of diabetes mellitus reported in patients taking rosuvastatin (2.8%) versus patients taking placebo (2.3%). Mean HbA1c was significantly increased by 0.1% in rosuvastatin-treated patients compared to placebo-treated patients. The number of patients with a HbA1c >6.5% at the end of the trial was significantly higher in rosuvastatin-treated versus placebo-treated patients [see Clinical Studies (14)].

Adverse reactions reported in ≥2% of patients and at a rate greater than placebo are shown in Table 4.

Table 4: Adverse Reactions Reported in ≥2% of Patients Treated with Rosuvastatin and > Placebo in the JUPITER Trial

Adverse Reactions | Placebo N=8,901; % | Rosuvastatin 20 mg N=8,901; %
Myalgia | 6.6 | 7.6
Arthralgia | 3.2 | 3.8
Constipation | 3 | 3.3
Diabetes mellitus | 2.3 | 2.8
Nausea | 2.3 | 2.4

Pediatric Patients with HeFH

In a 12-week controlled study in pediatric patients 10 to 17 years of age with HeFH with rosuvastatin 5 mg to 20 mg daily [see Use in Specific Populations (8.4) and Clinical Studies (14)], elevations in serum CK greater than 10 x ULN were observed more frequently in rosuvastatin-treated patients compared with patients receiving placebo. Four of 130 (3%) patients treated with rosuvastatin (2 treated with 10 mg and 2 treated with 20 mg) had increased CK greater than 10 x ULN, compared to 0 of 46 patients on placebo.

6.2 Postmarketing Experience

The following adverse reactions have been identified during postapproval use of rosuvastatin. Because these reactions are reported voluntarily from a population of uncertain size, it is not always possible to reliably estimate their frequency or establish a causal relationship to drug exposure.

Blood Disorders: thrombocytopenia

Hepatobiliary Disorders: hepatitis, jaundice, fatal and non-fatal hepatic failure

Musculoskeletal Disorders: arthralgia, rare reports of immune-mediated necrotizing myopathy associated with statin use

Nervous System Disorders: peripheral neuropathy, rare postmarketing reports of cognitive impairment (e.g., memory loss, forgetfulness, amnesia, memory impairment, and confusion) associated with the use of all statins. The reports are generally nonserious, and reversible upon statin discontinuation, with variable times to symptom onset (1 day to years) and symptom resolution (median of 3 weeks). There have been rare reports of new-onset or exacerbation of myasthenia gravis, including ocular myasthenia, and reports of recurrence when the same or a different statin was administered.

Psychiatric Disorders: depression, sleep disorders (including insomnia and nightmares)

Reproductive System and Breast Disorders: gynecomastia

Respiratory Disorders: interstitial lung disease

Skin and Subcutaneous Tissue Disorders: drug reaction with eosinophilia and systemic symptoms (DRESS), lichenoid drug eruption

7 DRUG INTERACTIONS

7.1 Drug Interactions that Increase the Risk of Myopathy and Rhabdomyolysis with EZALLOR SPRINKLE

Rosuvastatin is a substrate of CYP2C9 and transporters (such as OATP1B1, BCRP). Rosuvastatin plasma levels can be significantly increased with concomitant administration of inhibitors of CYP2C9 and transporters. Table 5 includes a list of drugs that increase the risk of myopathy and rhabdomyolysis when used concomitantly with EZALLOR SPRINKLE and instructions for preventing or managing them [see Warnings and Precautions (5.1) and Clinical Pharmacology (12.3)].

Table 5: Drug Interactions that Increase the Risk of Myopathy and Rhabdomyolysis with EZALLOR SPRINKLE

Cyclosporine
Clinical Impact: | Cyclosporine increased rosuvastatin exposure 7-fold. The risk of myopathy and rhabdomyolysis is increased with concomitant use of cyclosporine or gemfibrozil with EZALLOR SPRINKLE.
Intervention: | If used concomitantly, do not exceed a dose of EZALLOR SPRINKLE 5 mg once daily.
Teriflunomide
Clinical Impact: | Teriflunomide increased rosuvastatin exposure more than 2.5-fold. The risk of myopathy and rhabdomyolysis is increased with concomitant use.
Intervention: | In patients taking teriflunomide, do not exceed a dose of EZALLOR SPRINKLE 10 mg once daily.
Enasidenib
Clinical Impact: | Enasidenib increased rosuvastatin exposure more than 2.4-fold. The risk of myopathy and rhabdomyolysis is increased with concomitant use.
Intervention: | In patients taking enasidenib, do not exceed a dose of EZALLOR SPRINKLE 10 mg once daily.
Capmatinib
Clinical Impact: | Capmatinib increased rosuvastatin exposure more than 2.1-fold. The risk of myopathy and rhabdomyolysis is increased with concomitant use.
Intervention: | In patients taking capmatinib, do not exceed a dose of EZALLOR SPRINKLE 10 mg once daily.
Fostamatinib
Clinical Impact: | Fostamatinib increased rosuvastatin exposure more than 2-fold. The risk of myopathy and rhabdomyolysis is increased with concomitant use.
Intervention: | In patients taking fostamatinib, do not exceed a dose of EZALLOR SPRINKLE 20 mg once daily.
Febuxostat
Clinical Impact: | Febuxostat increased rosuvastatin exposure more than 1.9-fold. The risk of myopathy and rhabdomyolysis is increased with concomitant use.
Intervention: | In patients taking febuxostat, do not exceed a dose of EZALLOR SPRINKLE 20 mg once daily.
Gemfibrozil
Clinical Impact: | Gemfibrozil significantly increased rosuvastatin exposure and gemfibrozil may cause myopathy when given alone. The risk of myopathy and rhabdomyolysis is increased with concomitant use of gemfibrozil with EZALLOR SPRINKLE.
Intervention: | Avoid concomitant use of gemfibrozil with EZALLOR SPRINKLE. If used concomitantly, initiate EZALLOR SPRINKLE at 5 mg once daily and do not exceed a dose of EZALLOR SPRINKLE 10 mg once daily.
Tafamidis
Clinical Impact: | Tafamidis significantly increased rosuvastatin exposure and tafamidis may cause myopathy when given alone. The risk of myopathy and rhabdomyolysis is increased with concomitant use of tafamidis with EZALLOR SPRINKLE.
Intervention: | Avoid concomitant use of tafamidis with EZALLOR SPRINKLE. If used concomitantly, initiate EZALLOR SPRINKLE at 5 mg once daily and do not exceed a dose of EZALLOR SPRINKLE 20 mg once daily. Monitor for signs of myopathy and rhabdomyolysis if used concomitantly with EZALLOR SPRINKLE.
Anti-Viral Medications
Clinical Impact: | Rosuvastatin plasma levels were significantly increased with concomitant administration of many anti-viral drugs, which increases the risk of myopathy and rhabdomyolysis.
Intervention: | - Sofosbuvir/velpatasvir/voxilaprevir - Ledipasvir/sofosbuvir | Avoid concomitant use with EZALLOR SPRINKLE.
 | - Simeprevir - Dasabuvir/ombitasvir/paritaprevir/ritonavir - Elbasvir/grazoprevir - Sofosbuvir/velpatasvir - Glecaprevir/pibrentasvir - Atazanavir/ritonavir - Lopinavir/ritonavir | Initiate with EZALLOR SPRINKLE 5 mg; once daily, and do not exceed a dose of EZALLOR SPRINKLE 10; mg once daily.
Darolutamide
Clinical Impact: | Darolutamide increased rosuvastatin exposure more than 5-fold. The risk of myopathy and rhabdomyolysis is increased with concomitant use.
Intervention: | In patients taking darolutamide, do not exceed a dose of EZALLOR SPRINKLE 5 mg once daily.
Regorafenib
Clinical Impact: | Regorafenib increased rosuvastatin exposure and may increase the risk of myopathy.
Intervention: | In patients taking regorafenib, do not exceed a dose of EZALLOR SPRINKLE 10 mg once daily.
Fenofibrates (e.g., fenofibrate and fenofibric acid)
Clinical Impact: | Fibrates may cause myopathy when given alone. The risk of myopathy and rhabdomyolysis is increased with concomitant use of fibrates with EZALLOR SPRINKLE
Intervention: | Consider if the benefit of using fibrates concomitantly with EZALLOR SPRINKLE outweighs the increased risk of myopathy and rhabdomyolysis. If concomitant use is decided, monitor patients for signs and symptoms of myopathy, particularly during initiation of therapy and during upward dose titration of either drug.
Niacin
Clinical Impact: | Cases of myopathy and rhabdomyolysis have occurred with concomitant use of lipid-modifying doses (≥1 g/day) of niacin with EZALLOR SPRINKLE.
Intervention: | Consider if the benefit of using lipid-modifying doses (≥1 g/day) of niacin concomitantly with EZALLOR SPRINKLE outweighs the increased risk of myopathy and rhabdomyolysis. If concomitant use is decided, monitor patients for signs and symptoms of myopathy, particularly during initiation of therapy and during upward dose titration of either drug.
Colchicine
Clinical Impact: | Cases of myopathy and rhabdomyolysis have been reported with concomitant use of colchicine with EZALLOR SPRINKLE.
Intervention: | Consider if the benefit of using colchicine concomitantly with EZALLOR SPRINKLE outweighs the increased risk of myopathy and rhabdomyolysis. If concomitant use is decided, monitor patients for signs and symptoms of myopathy, particularly during initiation of therapy and during upward dose titration of either drug.
Ticagrelor
Clinical Impact: | Concomitant use of EZALLOR SPRINKLE and ticagrelor has been shown to increase rosuvastatin concentrations, which may result in increased risk of myopathy. Cases of myopathy and rhabdomyolysis have been reported in patients using both products concomitantly. Cases have occurred more frequently in patients taking 40 mg of rosuvastatin.
Intervention: | In patients taking concomitant ticagrelor, especially those with additional risk factors for myopathy and rhabdomyolysis, monitor patients for signs and symptoms of myopathy, particularly during initiation of therapy and during upward dose titration of EZALLOR SPRINKLE.

7.2 Drug Interactions that Decrease the Efficacy of EZALLOR SPRINKLE

Table 6 presents drug interactions that may decrease the efficacy of EZALLOR SPRINKLE and instructions for preventing or managing them.

Table 6: Drug Interactions that Decrease the Efficacy of EZALLOR SPRINKLE

Antacids
Clinical Impact: | Concomitant aluminum and magnesium hydroxide combination antacid administration decreased the mean exposure of rosuvastatin 50% [see Clinical Pharmacology (12.3)].
Intervention: | In patients taking antacid, administer EZALLOR SPRINKLE at least 2 hours before the antacid.

7.3 EZALLOR SPRINKLE Effects on Other Drugs

Table 7 presents EZALLOR SPRINKLE effect on other drugs and instructions for preventing or managing them.

Table 7: Rosuvastatin Effects on Other Drugs

Warfarin
Clinical Impact: | Rosuvastatin significantly increased the INR in patients receiving warfarin [see Clinical Pharmacology (12.3)].
Intervention: | In patients taking warfarin, obtain an INR before starting EZALLOR SPRINKLE and frequently enough after initiation, dose titration or discontinuation to ensure that no significant alteration in INR occurs. Once the INR is stable, monitor INR at regularly recommended intervals.

8 USE IN SPECIFIC POPULATIONS

8.1 Pregnancy

Risk Summary

Discontinue EZALLOR SPRINKLE when pregnancy is recognized. Alternatively, consider the ongoing therapeutic needs of the individual patient.

EZALLOR SPRINKLE decreases synthesis of cholesterol and possibly other biologically active substances derived from cholesterol; therefore, EZALLOR SPRINKLE may cause fetal harm when administered to pregnant patients based on the mechanism of action [see Clinical Pharmacology (12.1)]. In addition, treatment of hyperlipidemia is not generally necessary during pregnancy. Atherosclerosis is a chronic process and the discontinuation of lipid-lowering drugs during pregnancy should have little impact on the outcome of long-term therapy of primary hyperlipidemia for most patients.

Available data from case series and prospective and retrospective observational cohort studies over decades of use with statins in pregnant women have not identified a drug-associated risk of major congenital malformations. Published data from prospective and retrospective observational cohort studies with rosuvastatin use in pregnant women are insufficient to determine if there is a drug-associated risk of miscarriage (see Data).

In animal reproduction studies, no adverse developmental effects were observed in pregnant rats or rabbits orally administered rosuvastatin during the period of organogenesis at doses that resulted in systemic exposures equivalent to human exposures at the maximum recommended human dose (MRHD) of 40 mg/day, based on AUC and body surface area (mg/m^2), respectively (see Data).

The estimated background risk of major birth defects and miscarriage for the indicated population is unknown. In the U.S. general population, the estimated background risk of major birth defects and miscarriage in clinically recognized pregnancies is 2 to 4% and 15 to 20%, respectively.

Data

Human Data

A Medicaid cohort linkage study of 1,152 statin-exposed pregnant women compared to 886,996 controls

did not find a significant teratogenic effect from maternal use of statins in the first trimester of pregnancy,

after adjusting for potential confounders – including maternal age, diabetes mellitus, hypertension, obesity, and alcohol and tobacco use – using propensity score-based methods. The relative risk of congenital malformations between the group with statin use and the group with no statin use in the first trimester was 1.07 (95% confidence interval 0.85 to 1.37) after controlling for confounders, particularly preexisting diabetes mellitus. There were also no statistically significant increases in any of the organ-specific malformations assessed after accounting for confounders. In the majority of pregnancies, statin treatment was initiated prior to pregnancy and was discontinued at some point in the first trimester when pregnancy was identified. Study limitations include reliance on physician coding to define the presence of a malformation, lack of control for certain confounders such as body mass index, use of prescription dispensing as verification for the use of a statin, and lack of information on non-live births.

Animal Data

In female rats given 5, 15 and 50 mg/kg/day before mating and continuing through to gestation day 7 resulted in decreased fetal body weight (female pups) and delayed ossification at 50 mg/kg/day (10 times the human exposure at the MRHD dose of 40 mg/day based on AUC).

In pregnant rats given 2, 10 and 50 mg/kg/day of rosuvastatin from gestation day 7 through lactation day 21 (weaning), decreased pup survival occurred at 50 mg/kg/day (dose equivalent to 12 times the MRHD of 40 mg/day based body surface area).

In pregnant rabbits given 0.3, 1, and 3 mg/kg/day of rosuvastatin from gestation day 6 to day 18, decreased fetal viability and maternal mortality was observed at 3 mg/kg/day (dose equivalent to the MRHD of 40 mg/day based on body surface area).

Rosuvastatin crosses the placenta in rats and rabbits and is found in fetal tissue and amniotic fluid at 3% and 20%, respectively, of the maternal plasma concentration following a single 25 mg/kg oral gavage dose on gestation day 16 in rats. In rabbits, fetal tissue distribution was 25% of maternal plasma concentration after a single oral gavage dose of 1 mg/kg on gestation day 18.

8.2 Lactation

Risk Summary

Limited data from case reports in published literature indicate that rosuvastatin is present in human milk. There is no available information on the effects of the drug on the breastfed infant or the effects of the drug on milk production. Statins, including EZALLOR SPRINKLE, decrease cholesterol synthesis and possibly the synthesis of other biologically active substances derived from cholesterol and may cause harm to the breastfed infant.

Because of the potential for serious adverse reactions in a breastfed infant, based on the mechanism of action, advise patients that breastfeeding is not recommended during treatment with EZALLOR SPRINKLE [see Use in Specific Populations (8.1) and Clinical Pharmacology (12.1)].

8.4 Pediatric Use

The safety and effectiveness of rosuvastatin as an adjunct to diet to reduce LDL-C have been established in pediatric patients 8 years of age and older with HeFH. Use of rosuvastatin for this indication is based on one 12-week controlled trial with a 40-week open-label extension period in 176 pediatric patients 10 years of age and older with HeFH and one 2-year open-label, uncontrolled trial in 175 pediatric patients 8 years of age and older with HeFH [see Clinical Studies (14)]. In the 1-year trial with a 12-week controlled phase, there was no detectable effect of rosuvastatin on growth, weight, BMI (body mass index), or sexual maturation in patients aged 10 to 17 years.

The safety and effectiveness of rosuvastatin as an adjunct to other LDL-C-lowering therapies to reduce LDL-C have been established in pediatric patients 7 years of age and older with HoFH. Use of rosuvastatin for this indication is based on a randomized, placebo-controlled, cross-over study in 14 pediatric patients 7 years of age and older with HoFH [see Clinical Studies (14)].

The safety and effectiveness of rosuvastatin have not been established in pediatric patients younger than 8 years of age with HeFH, younger than 7 years of age with HoFH, or in pediatric patients with other types of hyperlipidemia (other than HeFH or HoFH).

8.5 Geriatric Use

Of the 10,275 patients in clinical studies with rosuvastatin, 3,159 (31%) were 65 years and older, and 698 (6.8%) were 75 years and older. No overall differences in safety or effectiveness were observed between these subjects and younger subjects.

Advanced age (≥65 years) is a risk factor for rosuvastatin-associated myopathy and rhabdomyolysis. Dose selection for an elderly patient should be cautious, recognizing the greater frequency of decreased hepatic, renal, or cardiac function, and of concomitant disease or other drug therapy and the higher risk of myopathy. Monitor geriatric patients receiving EZALLOR SPRINKLE for the increased risk of myopathy [see Warnings and Precautions (5.1)].

8.6 Renal Impairment

Rosuvastatin exposure is not influenced by mild to moderate renal impairment (CLcr ≥ 30 mL/min/1.73 m2). Exposure to rosuvastatin is increased to a clinically significant extent in patients with severe renal impairment (CLcr <30 mL/min/1.73 m2) who are not receiving hemodialysis [see Clinical Pharmacology (12.3)].

Renal impairment is a risk factor for myopathy and rhabdomyolysis. Monitor all patients with renal impairment for development of myopathy. In patients with severe renal impairment not on hemodialysis, the recommended starting dosage is 5 mg daily and should not exceed 10 mg daily [see Dosage and Administration (2.5) and Warnings and Precautions (5.1)].

8.7 Hepatic Impairment

EZALLOR SPRINKLE is contraindicated in patients with acute liver failure or decompensated cirrhosis. Chronic alcohol liver disease is known to increase rosuvastatin exposure. Patients who consume substantial quantities of alcohol and/or have a history of liver disease may be at increased risk for hepatic injury [see Contraindications (4), Warning and Precautions (5.3) and Clinical Pharmacology (12.3)].

8.8 Asian Patients

Pharmacokinetic studies have demonstrated an approximate 2-fold increase in median exposure to rosuvastatin in Asian subjects when compared with White controls. Adjust the EZALLOR SPRINKLE dosage in Asian patients [see Dosage and Administration (2.4) and Clinical Pharmacology (12.3)].

10 OVERDOSAGE

No specific antidotes for rosuvastatin are known. Hemodialysis does not significantly enhance clearance of rosuvastatin. In the event of overdose, consider contacting the Poison Help line (1- 800-222-1222) or a medical toxicologist for additional overdosage management recommendations.

11 DESCRIPTION

Rosuvastatin calcium is a 3-hydroxy-3-methylglutaryl coenzyme A (HMG CoA)-reductase inhibitor.

The chemical name for rosuvastatin calcium is bis[(E)-7-[4-(4-fluorophenyl)-6-isopropyl-2-[methyl(methylsulfonyl)amino] pyrimidin-5-yl]-(3R,5S)-3,5-dihydroxyhept-6-enoic acid] calcium salt with the following structural formula:
The molecular formula for rosuvastatin calcium is (C22H27FN3O6S)2·Ca and the molecular weight is 1,001.14. Rosuvastatin calcium is off-white to light yellow amorphous powder that is slightly soluble in water and methanol, and insoluble in ethanol. Rosuvastatin calcium is a hydrophilic compound with a partition coefficient (octanol/water) of 0.13 at pH of 7.

Each rosuvastatin capsule for oral use contains 5 mg, 10 mg, 20 mg, or 40 mg of rosuvastatin (present as 5.198 mg, 10.395 mg, 20.790 mg, or 41.580 mg of rosuvastatin calcium) in the form of granules with the following inactive ingredients: crospovidone, ferric oxide, hypromellose, magnesium oxide, mannitol, microcrystalline cellulose, polyethylene glycol 4000, silicon dioxide, and sodium citrate. The capsule shells have the following inactive ingredients: gelatin, sodium lauryl sulfate, titanium dioxide, and water. Additionally following colorants are used in capsules: FD&C Red 40 (5 mg), FD&C Blue 1 (5 mg, 10 mg, 20 mg), D&C Red 28 (5 mg, 10 mg), FD&C Red 3 (20 mg), and FD&C Green 3 (40 mg). The imprinting black ink contains black iron oxide, butyl alcohol, dehydrated alcohol, isopropyl alcohol, potassium hydroxide, propylene glycol, purified water, shellac, and strong ammonia solution.

12 CLINICAL PHARMACOLOGY

12.1 Mechanism of Action

Rosuvastatin is an inhibitor of HMG-CoA reductase, the rate-limiting enzyme that converts 3-hydroxy-3-methylglutaryl coenzyme A to mevalonate, a precursor of cholesterol.

12.2 Pharmacodynamics

Inhibition of HMG-CoA reductase by rosuvastatin accelerates the expression of LDL-receptors, followed by the uptake of LDL-C from blood to the liver, leading to a decrease in plasma LDL-C and total cholesterol. Sustained inhibition of cholesterol synthesis in the liver also decreases levels of very-low-density lipoproteins. The maximum LDL-C reduction of rosuvastatin is usually achieved by 4 weeks and is maintained after that.

12.3 Pharmacokinetics

Absorption

In clinical pharmacology studies in man, peak plasma concentrations of rosuvastatin were reached 3 to 5 hours following oral dosing. Both Cmax and AUC increased in approximate proportion to rosuvastatin dose. The absolute bioavailability of rosuvastatin is approximately 20%. The AUC of rosuvastatin does not differ following evening or morning drug administration.

Effect of food

Administration of rosuvastatin with food did not affect the AUC of rosuvastatin.

Distribution

Mean volume of distribution at steady-state of rosuvastatin is approximately 134 liters. Rosuvastatin is 88% bound to plasma proteins, mostly albumin. This binding is reversible and independent of plasma concentrations.

Elimination

Metabolism

Rosuvastatin is not extensively metabolized; approximately 10% of a radiolabeled dose is recovered as metabolite. The major metabolite is N-desmethyl rosuvastatin, which is formed principally by cytochrome P450 \ 2C9, and in vitro studies have demonstrated that N-desmethyl rosuvastatin has approximately one-sixth to one-half the HMG-CoA reductase inhibitory activity of the parent compound. Overall, greater than 90% of active plasma HMG-CoA reductase inhibitory activity is accounted for by the parent compound.

Excretion

Following oral administration, rosuvastatin and its metabolites are primarily excreted in the feces (90%).

After an intravenous dose, approximately 28% of total body clearance was via the renal route, and 72% by the hepatic route. The elimination half-life of rosuvastatin is approximately 19 hours.

Specific Populations

Geriatric Patients

There were no differences in plasma concentrations of rosuvastatin between the nonelderly and elderly populations (age ≥ 65 years).

Pediatric Patients

In a population pharmacokinetic analysis of two pediatric trials involving patients with HeFH 10 to 17 years of age and 8 to 17 years of age, respectively, rosuvastatin exposure appeared comparable to or lower than rosuvastatin exposure in adult patients.

Male and Female Patients

There were no differences in plasma concentrations of rosuvastatin between males and females.

Racial or Ethnic Groups

A population pharmacokinetic analysis revealed no clinically relevant differences in pharmacokinetics among White, Hispanic or Latino ethnicity, and Black or Afro-Caribbean groups. However, pharmacokinetic studies, including one conducted in the US, have demonstrated an approximate 2-fold elevation in median exposure (AUC and Cmax) in Asian subjects when compared with a White control group.

Patients with Renal Impairment

Mild to moderate renal impairment (CLcr ≥30 mL/min/1.73 m^2) had no influence on plasma concentrations of rosuvastatin. However, plasma concentrations of rosuvastatin increased to a clinically significant extent (about 3-fold) in patients with severe renal impairment (CLcr <30 mL/min/1.73 m^2) not receiving hemodialysis compared with healthy subjects (CLcr >80 mL/min/1.73 m^2).

Steady-state plasma concentrations of rosuvastatin in patients on chronic hemodialysis were approximately 50% greater compared with healthy volunteer subjects with normal renal function.

Patients with Hepatic Impairment

In patients with chronic alcohol liver disease, plasma concentrations of rosuvastatin were modestly increased.

In patients with Child-Pugh A disease, Cmax and AUC were increased by 60% and 5%, respectively, as compared with patients with normal liver function. In patients with Child-Pugh B disease, Cmax and AUC were increased 100% and 21%, respectively, compared with patients with normal liver function.

Drug Interaction Studies

Rosuvastatin clearance is not dependent on metabolism by cytochrome P450 3A4 to a clinically significant extent.

Rosuvastatin is a substrate for certain transporter proteins including the hepatic uptake transporter organic anion-transporting polyprotein 1B1 (OATP1B1) and efflux transporter breast cancer resistance protein (BCRP). Concomitant administration of rosuvastatin with medications that are inhibitors of these transporter proteins (e.g., cyclosporine, certain HIV protease inhibitors [see Dosage and Administration (2.6) and Drug Interactions (7.1)] and ticagrelor [see Drug Interactions (7.1)]) may result in increased rosuvastatin plasma concentrations.

Table 8: Effect of Coadministered Drugs on Rosuvastatin Systemic Exposure

Coadministered drug and dosing regimen | Rosuvastatin
 |  | Mean Ratio (ratio with/without coadministered drug) No Effect = 1
 | Dose (mg)^1 | Change in AUC | Change in Cmax
Sofosbuvir/velpatasvir/voxilaprevir (400 mg/100 mg/100 mg) + Voxilaprevir (100 mg) once daily for 15 days | 10 mg, single dose | 7.39^2 (6.68 to 8.18) ^3 | 18.88^2 (16.23 to 21.96) ^3
Cyclosporine - stable dose required (75 mg to 200 mg BID) | 10 mg, QD for 10 days | 7.1^2 | 11^2
Darolutamide 600 mg BID, 5 days | 5 mg, single dose | 5.2^2 | ~5^2
Regorafenib 160 mg QD, 14 days | 5 mg, single dose | 3.8^2 | 4.6^2
Atazanavir/ritonavir combination 300 mg/100 mg QD for 8 days | 10 mg | 3.1^2 | 7^2
Simeprevir 150 mg QD, 7 days | 10 mg, single dose | 2.8^2 (2.3 to 3.4)^3 | 3.2^2 (2.6 to 3.9)^3
Velpatasvir 100 mg once daily | 10 mg, single dose | 2.69^2 (2.46 to 2.94) ^3 | 2.61^2 (2.32 to 2.92)^3
Ombitasvir 25 mg/paritaprevir 150 mg/ ritonavir 100 mg + dasabuvir 400 mg BID | 5 mg, single dose | 2.59^2 (2.09 to 3.21) ^3 | 7.13^2 (5.11 to 9.96)^3
Teriflunomide | Not available | 2.51^2 | 2.65^2
Enasidenib 100 mg QD, 28 days | 10 mg, single dose | 2.44 | 3.66
Elbasvir 50 mg/grazoprevir 200mg once daily | 10 mg, single dose | 2.26^2 (1.89 to 2.69) ^3 | 5.49^2 (4.29 to 7.04)^3
Glecaprevir 400 mg/pibrentasvir 120 mg once daily | 5 mg, once daily | 2.15^2 (1.88 to 2.46) ^3 | 5.62^2 (4.80 to 6.59)^3
Lopinavir/ritonavir combination 400 mg/100 mg BID for 17 days | 20 mg, QD for 7 days | 2.1^2 (1.7 to 2.6)^3 | 5^2 (3.4 to 6.4)^3
Capmatinib 400 mg BID | 10 mg, single dose | 2.08^2 (1.56 to 2.76) ^3 | 3.04^2 (2.36 to 3.92)^3
Fostamatinib 100 mg BID | 20 mg, single dose | 1.96^2 (1.77 to 2.15) ^3 | 1.88^2 (1.69 to 2.09)^3
Febuxostat 120 mg QD for 4 days | 10 mg, single dose | 1.9^2 (1.5 to 2.5) ^3 | 2.1^2 (1.8 to 2.6)^3
Gemfibrozil 600 mg BID for 7 days | 80 mg | 1.9^2 (1.6 to 2.2)^3 | 2.2^2 (1.8 to 2.7)^3
Tafamidis 61 mg BID on Days 1 & 2, followed by QD on Days 3 to 9 | 10 mg | 1.97^2 (1.68 to 2.31)^3 | 1.86^2 (1.59 to 2.16)^3
Eltrombopag 75 mg QD, 5 days | 10 mg | 1.6 (1.4 to 1.7)^3 | 2 (1.8 to 2.3)^3
Darunavir 600 mg/ritonavir 100 mg BID, 7 days | 10 mg, QD for 7 days | 1.5 (1 to 2.1)^3 | 2.4 (1.6 to 3.6)^3
Tipranavir/ritonavir combination 500 mg/200 mg BID for 11 days | 10 mg | 1.4 (1.2 to 1.6)^3 | 2.2 (1.8 to 2.7)^3
Dronedarone 400 mg BID | 10 mg | 1.4
Itraconazole 200 mg QD, 5 days | 10 mg or 80 mg | 1.4 (1.2 to 1.6)^3 1.3 (1.1 to 1.4)^3 | 1.4 (1.2 to 1.5)^3 1.2 (0.9 to 1.4)^3
Ezetimibe 10 mg QD, 14 days | 10 mg, QD for 14 days | 1.2 (0.9 to 1.6)^3 | 1.2 (0.8 to 1.6)^3
Fosamprenavir/ritonavir 700 mg/100 mg BID for 7 days | 10 mg | 1.1 | 1.5
Fenofibrate 67 mg TID for 7 days | 10 mg | ↔ | 1.2 (1.1 to 1.3)^3
Rifampicin 450 mg QD, 7 days | 20 mg | ↔
Aluminum & magnesium hydroxide combination antacid Administered simultaneously Administered 2 hours apart | 40 mg 40 mg | 0.5^2 (0.4 to 0.5)^3 0.8 (0.7 to 0.9)^3 | 0.5^2 (0.4 to 0.6)^3 0.8 (0.7 to 1)^3
Ketoconazole 200 mg BID for 7 days | 80 mg | 1 (0.8 to 1.2)^3 | 1 (0.7 to 1.3)^3
Fluconazole 200 mg QD for 11 days | 80 mg | 1.1 (1 to 1.3)^3 | 1.1 (0.9 to 1.4)^3
Erythromycin 500 mg QID for 7 days | 80 mg | 0.8 (0.7 to 0.9)^3 | 0.7 (0.5 to 0.9)^3

QD= Once daily, BID= Twice daily, TID= Three times daily, QID= Four times daily

^1 Single dose unless otherwise noted.

^2 Clinically significant [see Dosage and Administration (2) and Warnings and Precautions (5)]

^3 Mean ratio with 90% CI (with/without coadministered drug, e.g., 1= no change, 0.7 = 30% decrease, 11=11 fold increase in exposure)

Table 9: Effect of Rosuvastatin Coadministration on Systemic Exposure to Other Drugs

Rosuvastatin Dosage Regimen | Coadministered Drug
 |  | Mean Ratio (ratio with/without coadministered drug) No Effect = 1
 | Name and Dose | Change in AUC | Change in Cmax
40 mg QD for 10 days | Warfarin^1 25 mg single dose | R-Warfarin 1 (1 to 1.1)^2 S-Warfarin 1.1 (1 to 1.1)^2 | R-Warfarin 1 (0.9 to 1)^2 S-Warfarin 1 (0.9 to 1.1)^2
40 mg QD for 12 days | Digoxin 0.5 mg single dose | 1 (0.9 to 1.2)^2 | 1 (0.9 to 1.2)^2
40 mg QD for 28 days | Oral Contraceptive (ethinyl estradiol 0.035 mg & norgestrel 0.18, 0.215 and 0.25 mg) QD for 21 Days | EE 1.3 (1.2 to 1.3)^2 NG 1.3 (1.3 to 1.4)^2 | EE 1.3 (1.2 to 1.3)^2 NG 1.2 (1.1 to 1.3)^2

EE = ethinyl estradiol, NG = norgestrel, QD = Once daily

^1 Clinically significant pharmacodynamic effects [see Drug Interactions (7.3)]

^2 Mean ratio with 90% CI (with/without coadministered drug, e.g., 1= no change, 0.7=30% decrease, 11=11-fold increase in exposure)

12.5 Pharmacogenomics

Disposition of rosuvastatin, involves OATP1B1 and other transporter proteins. Higher plasma concentrations of rosuvastatin have been reported in very small groups of patients (n=3 to 5) who have two reduced function alleles of the gene that encodes OATP1B1 (SLCO1B1 521T > C). The frequency of this genotype (i.e., SLCO1B1 521 C/C) is generally lower than 5% in most racial/ethnic groups. The impact of this polymorphism on efficacy and/or safety of rosuvastatin has not been clearly established.

13 NONCLINICAL TOXICOLOGY

13.1 Carcinogenesis, Mutagenesis, Impairment of Fertility

Carcinogenesis

In a 104-week carcinogenicity study in rats at dose levels of 2, 20, 60, or 80 mg/kg/day by oral gavage, the incidence of uterine stromal polyps was significantly increased in females at 80 mg/kg/day at systemic exposure 20 times the human exposure at 40 mg/day based on AUC. Increased incidence of polyps was not seen at lower doses.

In a 107-week carcinogenicity study in mice given 10, 60 or 200 mg/kg/day by oral gavage, an increased incidence of hepatocellular adenoma/carcinoma was observed at 200 mg/kg/day at systemic exposures 20 times the human exposure at 40 mg/day based on AUC. An increased incidence of hepatocellular tumors was not seen at lower doses.

Mutagenesis

Rosuvastatin was not mutagenic or clastogenic with or without metabolic activation in the Ames test with Salmonella typhimurium and Escherichia coli, the mouse lymphoma assay, and the chromosomal aberration assay in Chinese hamster lung cells. Rosuvastatin was negative in the in vivo mouse micronucleus test.

Impairment of Fertility

In rat fertility studies with oral gavage doses of 5, 15, 50 mg/kg/day, males were treated for 9 weeks prior to and throughout mating and females were treated 2 weeks prior to mating and throughout mating until gestation day 7. No adverse effect on fertility was observed at 50 mg/kg/day (systemic exposures up to 10 times the human exposure at 40 mg/day based on AUC). In testicles of dogs treated with rosuvastatin at 30 mg/kg/day for one month, spermatidic giant cells were seen. Spermatidic giant cells were observed in monkeys after 6-month treatment at 30 mg/kg/day in addition to vacuolation of seminiferous tubular epithelium. Exposures in the dog were 20 times and in the monkey 10 times the human exposure at 40 mg/day based on body surface area. Similar findings have been seen with other drugs in this class.

14 CLINICAL STUDIES

Primary Prevention of CV Disease

In the Justification for the Use of Statins in Primary Prevention: An Intervention Trial Evaluating Rosuvastatin (JUPITER) study, the effect of rosuvastatin on the occurrence of major CV disease events was assessed in 17,802 males (≥50 years) and females (≥60 years) who had no clinically evident CV disease, LDL-C levels <130 mg/dL and hsCRP levels ≥2 mg/L. The study population had an estimated baseline coronary heart disease risk of 11.6% over 10 years based on the Framingham risk criteria and included a high percentage of patients with additional risk factors such as hypertension (58%), low HDL-C levels (23%), cigarette smoking (16%), or a family history of premature CHD (12%). Patients had a median baseline LDL-C of 108 mg/dL and hsCRP of 4.3 mg/L. Patients were randomly assigned to placebo (n=8,901) or rosuvastatin 20 mg once daily (n=8,901) and were followed for a mean duration of 2 years. The JUPITER study was stopped early by the Data Safety Monitoring Board due to meeting predefined stopping rules for efficacy in rosuvastatin-treated subjects.

The primary end point was a composite end point consisting of the time-to-first occurrence of any of the following major CV events: CV death, nonfatal myocardial infarction, nonfatal stroke, hospitalization for unstable angina or an arterial revascularization procedure.

Rosuvastatin significantly reduced the risk of major CV events (252 events in the placebo group vs. 142 events in the rosuvastatin group) with a statistically significant (p<0.001) relative risk reduction of 44% and absolute risk reduction of 1.2% (see Figure 1). The risk reduction for the primary end point was consistent across the following predefined subgroups: age, sex, race, smoking status, family history of premature CHD, body mass index, LDL-C, HDL-C, and hsCRP levels.

Figure 1. Time to First Occurrence of Major CV Events in JUPITER

The individual components of the primary end point are presented in Figure 3. Rosuvastatin significantly reduced the risk of nonfatal myocardial infarction, nonfatal stroke, and arterial revascularization procedures. There were no significant treatment differences between the rosuvastatin and placebo groups for death due to CV causes or hospitalizations for unstable angina.

Rosuvastatin significantly reduced the risk of myocardial infarction (6 fatal events and 62 nonfatal events in placebo-treated subjects vs. 9 fatal events and 22 nonfatal events in rosuvastatin-treated subjects) and the risk of stroke (6 fatal events and 58 nonfatal events in placebo-treated subjects vs. 3 fatal events and 30 nonfatal events in rosuvastatin-treated subjects).

In a post-hoc subgroup analysis of JUPITER subjects (rosuvastatin=725, placebo=680) with a hsCRP ≥2 mg/L and no other traditional risk factors (smoking, BP ≥140/90 or taking antihypertensives, low HDL-C) other than age, after adjustment for high HDL-C, there was no significant treatment benefit with rosuvastatin treatment.

Figure 2. Major CV Events by Treatment Group in JUPITER

At one year, rosuvastatin increased HDL-C and reduced LDL-C, hsCRP, total cholesterol and serum triglyceride levels (p<0.001 for all versus placebo).

Primary Hyperlipidemia in Adults

Rosuvastatin reduces Total-C, LDL-C, ApoB, non-HDL-C, and TG, and increases HDL-C, in adult patients with hyperlipidemia and mixed dyslipidemia.

In a multicenter, double-blind, placebo-controlled study in patients with hyperlipidemia, rosuvastatin given as a single daily dose (5 to 40 mg) for 6 weeks significantly reduced Total-C, LDL-C, non-HDL-C, and ApoB, across the dose range (Table 10).

Table 10: Lipid-Modifying Effect of Rosuvastatin in Adult Patients with Hyperlipidemia (Adjusted Mean % Change from Baseline at Week 6)

Dose | N | Total-C | LDL-C | Non-HDL-C | ApoB | TG | HDL-C
Placebo | 13 | -5 | -7 | -7 | -3 | -3 | 3
Rosuvastatin 5 mg | 17 | -33 | -45 | -44 | -38 | -35 | 13
Rosuvastatin 10 mg | 17 | -36 | -52 | -48 | -42 | -10 | 14
Rosuvastatin 20 mg | 17 | -40 | -55 | -51 | -46 | -23 | 8
Rosuvastatin 40 mg | 18 | -46 | -63 | -60 | -54 | -28 | 10

Rosuvastatin was compared with the statins (atorvastatin, simvastatin, and pravastatin) in a multicenter, open-label, dose-ranging study of 2,240 patients with hyperlipidemia or mixed dyslipidemia. After randomization, patients were treated for 6 weeks with a single daily dose of either rosuvastatin, atorvastatin, simvastatin, or pravastatin (see Figure 3 and Table 11).

Figure 3. Percent LDL-C Change by Dose of Rosuvastatin, Atorvastatin, Simvastatin, and Pravastatin at Week 6 in Adult Patients with Hyperlipidemia or Mixed Dyslipidemia

Box plots are a representation of the 25th, 50th, and 75th percentile values, with whiskers representing the 10th and 90th percentile values. Mean baseline LDL-C: 189 mg/dL

Table 11: Percent Change in LDL-C by Dose of Rosuvastatin, Atorvastatin, Simvastatin, and Pravastatin From Baseline to Week 6 (LS Mean^1) in Adult Patients with Hyperlipidemia or Mixed Dyslipidemia (Sample Sizes Ranging from 156 to 167 Patients Per Group)

 | Treatment Daily Dose
Treatment | 10 mg | 20 mg | 40 mg | 80 mg
Rosuvastatin | -46^2 | -52^3 | -55^4 | ---
Atorvastatin | -37 | -43 | -48 | -51
Simvastatin | -28 | -35 | -39 | -46
Pravastatin | -20 | -24 | -30 | ---

^1 Corresponding standard errors are approximately 1.

^2Rosuvastatin 10 mg reduced LDL-C significantly more than atorvastatin 10 mg; pravastatin 10 mg, 20 mg, and 40 mg; simvastatin 10 mg, 20 mg, and 40 mg. (p<0.002)

^3Rosuvastatin 20 mg reduced LDL-C significantly more than atorvastatin 20 mg and 40 mg; pravastatin 20 mg and 40 mg; simvastatin 20 mg, 40 mg, and 80 mg. (p<0.002)

^4Rosuvastatin 40 mg reduced LDL-C significantly more than atorvastatin 40 mg; pravastatin 40 mg; simvastatin 40 mg, and 80 mg. (p<0.002)

Slowing of the Progression of Atherosclerosis

In the Measuring Effects on Intima Media Thickness: an Evaluation Of Rosuvastatin 40 mg (METEOR) study, the effect of therapy with rosuvastatin on carotid atherosclerosis was assessed by B-mode ultrasonography in patients with elevated LDL-C, at low risk (Framingham risk <10% over ten years) for symptomatic coronary artery disease and with subclinical atherosclerosis as evidenced by carotid intimal-medial thickness (cIMT). In this double-blind, placebo-controlled clinical study 984 adult patients were randomized (of whom 876 were analyzed) in a 5:2 ratio to rosuvastatin 40 mg or placebo once daily. Ultrasonograms of the carotid walls were used to determine the annualized rate of change per patient from baseline to two years in mean maximum cIMT of 12 measured segments. The estimated difference in the rate of change in the maximum cIMT analyzed over all 12 carotid artery sites between patients treated with rosuvastatin and placebo-treated patients was -0.0145 mm/year (95% CI –0.0196, –0.0093; p<0.0001).

The annualized rate of change from baseline for the placebo group was +0.0131 mm/year (p<0.0001). The annualized rate of change from baseline for the group treated with rosuvastatin was -0.0014 mm/year (p=0.32).

At an individual patient level in the group treated with rosuvastatin, 52.1% of patients demonstrated an absence of disease progression (defined as a negative annualized rate of change), compared to 37.7% of patients in the placebo group.

HeFH in Adults

In a study of adult patients with HeFH (baseline mean LDL of 291 mg/dL), patients were randomized to rosuvastatin 20 mg or atorvastatin 20 mg. The dose was increased at 6-week intervals. Significant LDL-C reductions from baseline were seen at each dose in both treatment groups (see Table 12).

Table 12: LDL-C Percent Change from Baseline

 |  | Rosuvastatin (n=435) LS Mean^1 (95% CI) | Atorvastatin (n=187) LS Mean^1 (95% CI)
Week 6 | 20 mg | -47% (-49%, -46%) | -38% (-40%, -36%)
Week 12 | 40 mg | -55% (-57%, -54%) | -47% (-49%, -45%)
Week 18 | 80 mg | NA | -52% (-54%, -50%)

^1 LS Means are least square means adjusted for baseline LDL-C

HeFH in Pediatric Patients

In a double-blind, randomized, multicenter, placebo-controlled, 12-week study, 176 (97 male and 79 female) pediatric patients with HeFH were randomized to rosuvastatin 5 mg, 10 mg or 20 mg or placebo daily. Patients ranged in age from 10 to 17 years (median age of 14 years) with approximately 30% of the patients 10 to 13 years and approximately 17%, 18%, 40%, and 25% at Tanner stages II, III, IV, and V, respectively. Females were at least 1-year postmenarche. Mean LDL-C at baseline was 233 mg/dL (range of 129 to 399). The 12-week double-blind phase was followed by a 40 week open label dose-titration phase, where all patients (n=173) received 5 mg, 10 mg or 20 mg rosuvastatin daily.

Rosuvastatin significantly reduced LDL-C (primary end point), total cholesterol and ApoB levels at each dose compared to placebo. Results are shown in Table 13 below.

Table 13: Lipid-Modifying Effects of Rosuvastatin in Pediatric Patients 10 to 17 years of Age with HeFH (Least-Squares Mean Percent Change from Baseline To Week 12)

Dose (mg) | N | LDL-C | HDL-C | Total-C | TG^1 | ApoB
Placebo | 46 | -1% | +7% | 0% | -7% | -2%
5 | 42 | -38% | +4%^2 | -30% | -13%^2 | -32%
10 | 44 | -45% | +11%^2 | -34% | -15%^2 | -38%
20 | 44 | -50% | +9%^2 | -39% | 16%^2 | -41%

^1 Median percent change

^2 Difference from placebo not statistically significant

Rosuvastatin was also studied in a two year open-label, uncontrolled, titration-to-goal trial that included 175 pediatric patients with HeFH who were 8 to 17 years old (79 males and 96 females). All patients had a documented genetic defect in the LDL receptor or in ApoB. Approximately 89% were White, 7% were Asian, 1% were Black or African American, and fewer than 1% were Hispanic or Latino ethnicity. Mean LDL-C at baseline was 236 mg/dL. Fifty-eight (33%) patients were prepubertal at baseline. The starting rosuvastatin dosage for all pediatric patients was 5 mg once daily. Pediatric patients aged 8 to less than 10 years (n=41 at baseline) could titrate to a maximum dosage of 10 mg once daily, and pediatric patients aged 10 to 17 years could titrate to a maximum dosage of 20 mg once daily.

The reductions in LDL-C from baseline were generally consistent across age groups within the trial as well as with previous experience in both adult and pediatric controlled trials.

Ho FH in Adult and Pediatric Patients

In an open-label, forced-titration study, HoFH patients (n=40, 8 to 63 years) were evaluated for their response to rosuvastatin 20 to 40 mg titrated at a 6-week interval. In the overall population, the mean LDL-C reduction from baseline was 22%. About one-third of the patients benefited from increasing their dose from 20 mg to 40 mg with further LDL-C lowering of greater than 6%. In the 27 patients with at least a 15% reduction in LDL-C, the mean LDL-C reduction was 30% (median 28% reduction). Among 13 patients with an LDL-C reduction of <15%, 3 had no change or an increase in LDL-C. Reductions in LDL-C of 15% or greater were observed in 3 of 5 patients with known receptor negative status.

Ho FH in Pediatric Patients

Rosuvastatin was studied in a randomized, double-blind, placebo-controlled, multicenter, cross-over study in 14 pediatric patients with HoFH. The study included a 4-week dietary lead-in phase during which patients received rosuvastatin 10 mg daily, a cross-over phase that included two 6-week treatment periods with either rosuvastatin 20 mg or placebo in random order, followed by a 12-week open-label phase during which all patients received rosuvastatin 20 mg. Patients ranged in age from 7 to 15 years of age (median 11 years), 50% were male, 71% were White, 21% were Asian, 7% were Black or African American, and no patients were of Hispanic or Latino ethnicity. Fifty percent were on apheresis therapy and 57% were taking ezetimibe. Patients who entered the study on apheresis therapy or ezetimibe continued the treatment throughout the entire study. Mean LDL-C at baseline was 416 mg/dL (range 152 to 716 mg/dL). A total of 13 patients completed both treatment periods of the randomized crossover phase; one patient withdrew consent due to inability to have blood drawn during the cross-over phase.

Rosuvastatin 20 mg significantly reduced LDL-C, total cholesterol, ApoB, and non-HDL-C compared to placebo (see Table 14).

Table 14: Lipid-Modifying Effects of Rosuvastatin in Pediatric Patients 7 to 15 years of Age with HoFH After 6 Weeks

 | Placebo (N=13) | Rosuvastatin 20 mg (N=13) | Percent difference (95% CI)
LDL-C (mg/dL) | 481 | 396 | -22.3% (-33.5, -9.1)^1
Total-C (mg/dL) | 539 | 448 | -20.1% (-29.7, -9.1)^2
Non-HDL-C (mg/dL) | 505 | 412 | -22.9% (-33.7, -10.3)^2
ApoB (mg/dL) | 268 | 235 | -17.1% (-29.2, -2.9)^3

% Difference estimates are based on transformations of the estimated mean difference in log LDL measurements between rosuvastatin and placebo using a mixed model adjusted for study period

^1 p=0.005, ^2 p=0.003, ^3 p=0.024

Primary Dysbetalipoproteinemia in Adults

In a randomized, multicenter, double-blind cross-over study, 32 adult patients (27 with є2/є2 and 4 with apo E mutation [Arg145Cys] with primary dysbetalipoproteinemia entered a 6-week dietary lead-in period on the NCEP Therapeutic Lifestyle Change (TLC) diet.

Following dietary lead-in, patients were randomized to a sequence of treatments for 6 weeks each: rosuvastatin 10 mg followed by rosuvastatin 20 mg or rosuvastatin 20 mg followed by rosuvastatin 10 mg. Rosuvastatin reduced non-HDL-C (primary end point) and circulating remnant lipoprotein levels. Results are shown in the table below.

Table 15: Lipid-Modifying Effects of Rosuvastatin 10 mg and 20 mg in Adult Patients with Primary Dysbetalipoproteinemia (Type III hyperlipoproteinemia) After Six Weeks by Median Percent Change (95% CI) from Baseline (N=32)

 | Median at Baseline (mg/dL) | Median percent change from baseline (95% CI) Rosuvastatin 10 mg | Median percent change from baseline (95% CI) Rosuvastatin 20 mg
Total-C | 342.5 | -43.3 (-46.9, -37.5) | -47.6 (-51.6,-42.8)
Triglycerides | 503.5 | -40.1 (-44.9, -33.6) | -43 (-52.5, -33.1)
Non-HDL-C | 294.5 | -48.2 (-56.7, -45.6) | -56.4 (-61.4, -48.5)
VLDL-C + IDL-C | 209.5 | -46.8 (-53.7, -39.4) | -56.2 (-67.7, -43.7)
LDL-C | 112.5 | -54.4 (-59.1, -47.3) | -57.3 (-59.4, -52.1)
HDL-C | 35.5 | 10.2 (1.9, 12.3) | 11.2 (8.3, 20.5)
RLP-C | 82 | -56.4 (-67.1, -49) | -64.9 (-74, -56.6)
Apo-E | 16 | -42.9 (-46.3, -33.3) | -42.5 (-47.1, -35.6)

Hypertriglyceridemia in Adults

In a double-blind, placebo-controlled study in adult patients with baseline TG levels from 273 to 817 mg/dL, rosuvastatin given as a single daily dose (5 mg to 40 mg) over 6 weeks significantly reduced serum TG levels (see Table 16).

Table 16: Lipid-Modifying Effect of Rosuvastatin in Adult Patients with Primary Hypertriglyceridemia After Six Weeks by Median (Min, Max) Percent Change from Baseline to Week 6

Dose | Placebo (n=26) | Rosuvastatin 5 mg (n=25) | Rosuvastatin 10 mg (n=23) | Rosuvastatin 20 mg (n=27) | Rosuvastatin 40 mg (n=25)
Triglycerides | 1 (-40, 72) | -21 (-58, 38) | -37 (-65, 5) | -37 (-72, 11) | -43 (-80, -7)
Non-HDL-C | 2 (-13, 19) | -29 (-43, -8) | -49 (-59, -20) | -43 (-74, 12) | -51 (-62, -6)
Total-C | 1 (-13, 17) | -24 (-40, -4) | -40 (-51, -14) | -34 (-61, -11) | -40 (-51, -4)
LDL-C | 5 (-30, 52) | -28 (-71, 2) | -45 (-59, 7) | -31 (-66, 34) | -43 (-61, -3)
HDL-C | -3 (-25, 18) | 3 (-38, 33) | 8 (-8, 24) | 22 (-5, 50) | 17 (-14, 63)

16 HOW SUPPLIED/STORAGE AND HANDLING

EZALLOR SPRINKLE (rosuvastatin) capsules 5 mg are hard gelatin capsule, Size “3” pink cap/off white body, imprinted axially with “984” on cap and body in black ink filled with yellow colored granules. They are available as follows:

Bottles of 30’s with Child Resistant Closure …………………. NDC 47335-984-83

Bottles of 90’s with Child Resistant Closure …………………. NDC 47335-984-81

Unit-dose blister pack of 30 (3 × 10) capsules ……………….. NDC 47335-984-64

EZALLOR SPRINKLE (rosuvastatin) capsules 10 mg are hard gelatin capsule, Size “3” purple cap/off white body, imprinted axially with “985” on cap and body in black ink filled with yellow colored granules. They are available as follows:

Bottles of 30’s with Child Resistant Closure …………………. NDC 47335-985-83

Bottles of 90’s with Child Resistant Closure …………………. NDC 47335-985-81

Unit-dose blister pack of 30 (3 × 10) capsules ……………….. NDC 47335-985-64

EZALLOR SPRINKLE (rosuvastatin) capsules 20 mg are hard gelatin capsule, Size “1” blue cap/off white body, imprinted axially with “986” on cap and body in black ink filled with yellow colored granules. They are available as follows:

Bottles of 30’s with Child Resistant Closure …………………. NDC 47335-986-83

Bottles of 90’s with Child Resistant Closure …………………. NDC 47335-986-81

Unit-dose blister pack of 30 (3 × 10) capsules ……………….. NDC 47335-986-64

EZALLOR SPRINKLE (rosuvastatin) capsules 40 mg are hard gelatin capsule, Size “0el” green cap/white body, imprinted axially with “987” on cap and body in black ink filled with yellow colored granules. They are available as follows:

Bottles of 30’s with Child Resistant Closure …………………. NDC 47335-987-83

Bottles of 90’s with Child Resistant Closure …………………. NDC 47335-987-81

Unit-dose blister pack of 30 (3 × 10) capsules ……………….. NDC 47335-987-64

Storage

Store EZALLOR SPRINKLE (rosuvastatin) capsules at 20º to 25ºC (68º to 77ºF); excursions permitted between 15° and 30°C (59° and 86°F) [see USP Controlled Room Temperature].

Protect from moisture.

17 PATIENT COUNSELING INFORMATION

Advise the patient to read the FDA-approved patient labeling (Patient Information and Instructions for Use).

Myopathy and Rhabdomyolysis

Advise patients that EZALLOR SPRINKLE may cause myopathy and rhabdomyolysis. Inform patients that the risk is also increased when taking certain types of medication and they should discuss all medication, both prescription and over-the-counter, with their healthcare provider. Instruct patients to promptly report any unexplained muscle pain, tenderness or weakness particularly if accompanied by malaise or fever [see Warnings and Precautions (5.1), and Drug Interactions (7.1)].

Hepatic Dysfunction

Inform patients that EZALLOR SPRINKLE may cause liver enzyme elevations and possibly liver failure. Advise patients to promptly report fatigue, anorexia, right upper abdominal discomfort, dark urine or jaundice [see Warnings and Precautions (5.3)].

Increases in HbA1c and Fasting Serum Glucose Levels

Inform patients that increases in HbA1c and fasting serum glucose levels may occur with EZALLOR SPRINKLE. Encourage patients to optimize lifestyle measures, including regular exercise, maintaining a healthy body weight, and making healthy food choices [see Warnings and Precautions (5.5)].

Pregnancy

Advise pregnant patients and patients who can become pregnant of the potential risk to a fetus. Advise patients to inform their healthcare provider of a known or suspected pregnancy to discuss if EZALLOR SPRINKLE should be discontinued [see Use in Specific Populations (8.1)].

Lactation

Advise patients that breastfeeding during treatment with EZALLOR SPRINKLE is not recommended [see Use in Specific Populations (8.2)].

Concomitant Use of Antacids

When taking EZALLOR SPRINKLE with an aluminum and magnesium hydroxide combination antacid, administer EZALLOR SPRINKLE at least 2 hours before the antacid [see Drug Interactions (7.2)].

Missed Doses

If a dose is missed, advise patients not to take an extra dose. Just resume the usual schedule [see Dosage and Administration (2.1)].

Distributed by:
Sun Pharmaceutical Industries, Inc.
Cranbury, NJ 08512

Manufactured by:
Sun Pharmaceutical Industries Limited
Halol-Baroda Highway,
Halol-389 350, Gujarat, India.

FDA-05
EZALLOR SPRINKLE is a registered trademark of Sun Pharmaceutical Industries Limited.

PATIENT INFORMATION

EZALLOR SPRINKLE® [Ez-Aah-Lor Spr-En-Kle]
(rosuvastatin) capsules, for oral use

Read this Patient Information carefully before you start taking EZALLOR SPRINKLE and each time you get a refill. If you have any questions about EZALLOR SPRINKLE, ask your healthcare provider. Only your healthcare provider can determine if EZALLOR SPRINKLE is right for you.

What is EZALLOR SPRINKLE?

EZALLOR SPRINKLE is a prescription medicine that contains a cholesterol-lowering medicine called rosuvastatin.

- EZALLOR SPRINKLE is used:
  - to reduce the risk of major adverse cardiovascular (CV) events, such as death from CV disease, heart attack, stroke, or the need for procedures to improve blood flow to the heart called arterial revascularization, in adults who do not have known heart disease but do have certain additional risk factors.
- along with diet to:
- lower the level of low-density lipoprotein (LDL-C) cholesterol or “bad” cholesterol in adults with primary hyperlipidemia.
- slow the buildup of fatty deposits (plaque) in the walls of blood vessels.
- treat adults and children 8 years of age and older with high blood cholesterol due to heterozygous familial hypercholesterolemia (HeFH) (an inherited condition that causes high levels of LDL-C).
  - along with other cholesterol lowering treatments or alone if such treatments are unavailable in adults and children 7 years of age and older with homozygous familial hypercholesterolemia (HoFH) (an inherited condition that causes high levels of LDL-C).
    - along with diet for the treatment of adults with:
    - primary dysbetalipoproteinemia (an inherited condition that causes high levels of cholesterol and fat).
    - hypertriglyceridemia.

It is not known if EZALLOR SPRINKLE is safe and effective in children younger than 8 years of age with HeFH or children younger than 7 years of age with HoFH or in children with other types of hyperlipidemias (other than HeFH or HoFH).

Do not take EZALLOR SPRINKLE if you:

- have liver problems.
- are allergic to rosuvastatin or any of the ingredients in EZALLOR SPRINKLE. See the end of this leaflet for a complete list of ingredients in EZALLOR SPRINKLE.

Before you take EZALLOR SPRINKLE, tell your healthcare provider about all of your medical conditions, including if you:

- have unexplained muscle aches or weakness.
- have or have had kidney problems.
- have or have had liver problems.
- drink more than 2 glasses of alcohol daily.
- have thyroid problems.
- are of Asian descent.

- are pregnant or think you may be pregnant, or are planning to become pregnant. If you become pregnant while taking EZALLOR SPRINKLE, call your healthcare provider right away to discuss your EZALLOR SPRINKLE treatment.
- are breastfeeding. EZALLOR SPRINKLE can pass into your breast milk and may harm your baby. Talk to your healthcare provider about the best way to feed your baby if you take EZALLOR SPRINKLE. Do not breastfeed while taking EZALLOR SPRINKLE.

Tell your healthcare provider about all the medicines you take, including prescription and over-the-counter medicines, vitamins, and herbal supplements. Tell your healthcare provider who prescribes EZALLOR SPRINKLE if another healthcare provider increases the dose of another medicine you are taking. EZALLOR SPRINKLE may affect the way other medicines work, and other medicines may affect how EZALLOR SPRINKLE works.

Especially tell your healthcare provider if you take:

- coumarin anticoagulants (medicines that prevent blood clots, such as warfarin)
- antacids (medicines you take for heartburn that contain aluminum and magnesium hydroxide

Taking EZALLOR SPRINKLE with certain medicines may increase the risk of muscle problems.

Especially tell your healthcare provider if you take:

- cyclosporine (a medicine for your immune system)
- teriflunomide (a medicine used to treat relapsing remitting multiple sclerosis)
- enasidenib (a medicine used to treat acute myeloid leukemia)
- capmatinib (a medicine for the treatment of non-small cell lung cancer)
- fostamatinib (a medicine used to treat low platelet counts)
- febuxostat (a medicine used to treat and prevent high blood levels of uric acid)
- gemfibrozil (a fibric acid medicine for lowering cholesterol)
- tafamidis [used to treat cardiomyopathy (enlarged and thickened heart muscle)]
- anti-viral medicines including certain HIV or hepatitis C virus medicines such as:
-
  - lopinavir, ritonavir, fosamprenavir, tipranavir, atazanavir, simeprevir
  - combination of
  -
    - sofosbuvir/velpatasvir/voxilaprevir
    - dasabuvir/ombitasvir/paritaprevir/ritonavir
    - elbasvir/grazoprevir
    - sofosbuvir/velpatasvir
    - glecaprevir/pibrentasvir and
  - all other combinations with ledipasvir including ledipasvir/sofosbuvir
- darolutamide (a medicine for the treatment of prostate cancer)
- regorafenib (a medicine used to treat cancer of the colon and rectum)
- fibric acid derivatives (such as fenofibrate)
- ticagrelor (helps reduce the chance of a blood clot formation that can block a blood vessel)
- niacin or nicotinic acid
- colchicine (a medicine used to treat gout)

Ask your healthcare provider or pharmacist for a list of these medicines if you are not sure. Know the medicines you take. Keep a list of them to show your healthcare provider and pharmacist when you get new medicine.

How should I take EZALLOR SPRINKLE?

- Take EZALLOR SPRINKLE exactly as your healthcare provider tells you to take it.
- Take EZALLOR SPRINKLE, by mouth, 1 time each day, with or without food. Swallow the capsule whole.
- Do not crush or chew EZALLOR SPRINKLE
- EZALLOR SPRINKLE can be taken at any time of day, with or without food.
- If you have trouble swallowing a whole capsule, you can open the capsule and take the contents with soft food (applesauce, or chocolate- or vanilla-flavored pudding). See the “Instructions for Use” at the end of this Patient Package Information for instructions on how to take EZALLOR SPRINKLE by mouth.
- See the “Instructions for Use” at the end of this Patient Package Information for instructions on how to mix and give EZALLOR SPRINKLE through a nasogastric tube.
- Do not change your dose or stop EZALLOR SPRINKLE without talking to your healthcare provider, even if you are feeling well.
- Your healthcare provider may do blood tests to check your cholesterol levels before and during your treatment with EZALLOR SPRINKLE. Your healthcare provider may change your dose of EZALLOR SPRINKLE if needed.
- While taking EZALLOR SPRINKLE, continue to follow your cholesterol-lowering diet and to exercise as your healthcare provider told you to.
- If you take a medicine called an antacid that contains a combination of aluminum and magnesium hydroxide, take EZALLOR SPRINKLE at least 2 hours before you take the antacid.
- If you miss a dose of EZALLOR SPRINKLE, take your next dose at your normal scheduled time. Do not take an extra dose of EZALLOR SPRINKLE.
- In case of an overdose, get medical help or contact a live Poison Center expert right away at 1-800-222-1222. Advice is also available online at poisonhelp.org.

What are the possible side effects of EZALLOR SPRINKLE?

EZALLOR SPRINKLE may cause serious side effects, including:

- Muscle pain, tenderness and weakness (myopathy). Muscle problems, including muscle breakdown, can be serious in some people and rarely cause kidney damage that can lead to death. Tell your healthcare provider right away if:
  - you have unexplained muscle pain, tenderness, or weakness, especially if you have a fever or feel more tired than usual, while you take EZALLOR SPRINKLE.
  - you have muscle problems that do not go away even after your healthcare provider has told you to stop taking EZALLOR SPRINKLE. Your healthcare provider may do further tests to diagnose the cause of your muscle problems.

Your chances of getting muscle problems are higher if you:

- are taking certain other medicines while you take EZALLOR SPRINKLE (see “Especially tell your healthcare provider if you take”)
- are 65 years of age or older
- are of Asian descent
- have thyroid problems (hypothyroidism) that are not controlled
- have kidney problems
- are taking higher doses of EZALLOR SPRINKLE
- Liver problems. Your healthcare provider may do blood tests to check your liver before you start taking EZALLOR SPRINKLE and if you have symptoms of liver problems while you take EZALLOR SPRINKLE. Call your healthcare provider right away if you have any of the following symptoms of liver problems:
  - feel unusually tired or weak
  - loss of appetite
  - upper belly pain
  - dark urine
  - yellowing of your skin or the whites of your eyes
- Protein and blood in the urine. EZALLOR SPRINKLE may cause you to have protein and blood in your urine. If you develop protein or blood in your urine, your healthcare provider may decrease your dose of EZALLOR SPRINKLE.
- Increase in blood sugar (glucose) levels. EZALLOR SPRINKLE may cause an increase in your blood sugar levels.

The most common side effects may include headache, nausea, muscle aches and pains, weakness, and constipation.

Tell your healthcare provider if you have any side effect that bothers you or that does not go away.

For more information, ask your healthcare provider or pharmacist.

Call your doctor for medical advice about side effects. You may report side effects to FDA at 1-800-FDA-1088.

How should I store EZALLOR SPRINKLE?

- Store EZALLOR SPRINKLE at room temperature between 68ºF to 77ºF (20ºC to 25ºC).
- Store in a dry place.

Keep EZALLOR SPRINKLE and all medicines out of the reach of children.

General Information about the safe and effective use of EZALLOR SPRINKLE.
Medicines are sometimes prescribed for purposes other than those listed in a Patient Information leaflet. Do not use EZALLOR SPRINKLE for a condition for which it was not prescribed. Do not give EZALLOR SPRINKLE to other people, even if they have the same medical condition you have. It may harm them.
You can ask your pharmacist or healthcare provider for information about EZALLOR SPRINKLE that is written for health professionals.

What are the Ingredients in EZALLOR SPRINKLE?
Active Ingredient: rosuvastatin as rosuvastatin calcium
Inactive Ingredients: crospovidone, ferric oxide, hypromellose, magnesium oxide, mannitol, microcrystalline cellulose, polyethylene glycol 4000, silicon dioxide, and sodium citrate.
Capsule shell: gelatin, sodium lauryl sulfate, titanium dioxide, water and the following colorants: FD & C Red 40 (5 mg), FD & C Blue 1 (5 mg, 10 mg, 20 mg), D & C Red 28 (5 mg, 10 mg), FD & C Red 3 (20 mg), and FD & C Green 3 (40 mg).The imprinting black ink contains black iron oxide, butyl alcohol, dehydrated alcohol, isopropyl alcohol, potassium hydroxide propylene glycol, purified water, shellac and strong ammonia solution.
Distributed by:
Sun Pharmaceutical Industries, Inc.
Cranbury, NJ 08512
Manufactured by:
Sun Pharmaceutical Industries Limited,
Halol-Baroda Highway, Halol-389 350, Gujarat, India.
EZALLOR SPRINKLE is a registered trademark of Sun Pharmaceutical Industries Limited.
For more information, call 1- 1-800-818-4555.
FDA-05
This Patient Information has been approved by the U.S. Food and Drug Administration
Issued: 02/2025

INSTRUCTIONS FOR USE

EZALLOR SPRINKLE® [Ez-Aah-Lor Spr-En-Kle]

(rosuvastatin) capsules, for oral use

Taking EZALLOR SPRINKLE with soft food (applesauce, or chocolate- or vanilla-flavored pudding):

For people who have difficulty in swallowing capsules, EZALLOR SPRINKLE may be given with soft food (applesauce, or chocolate- or vanilla-flavored pudding) as follows:

1. Carefully open the EZALLOR SPRINKLE capsule.
2. Sprinkle the entire contents of the capsule onto at least 1 teaspoonful (5 mL) of soft food (such as applesauce, or chocolate- or vanilla-flavored pudding).
3. Stir the mixture and for 10 to 15 seconds.
4. Swallow the entire mixture within 60 minutes of mixing. Do not chew the mixture.
5. Do not save the mixture for later use. Discard the unused portion immediately.

Giving EZALLOR SPRINKLE through a nasogastric tube (NG tube) 16 French or larger, as prescribed by your doctor:

For people who have a nasogastric tube in place, EZALLOR SPRINKLE may be given as follows:

1. Remove the plunger from 60 mL catheter tipped syringe.
2. Carefully open the EZALLOR SPRINKLE capsule and empty the granules into catheter tipped syringe barrel.
3. Add 40 mL of water to the granules that are inside of the catheter tipped syringe barrel. Do not use with liquids other than water.
4. Replace the plunger and shake the catheter tipped syringe well for 15 seconds. The granules in EZALLOR SPRINKLE capsule may start dissolving which is acceptable.
5. Attach the catheter tipped syringe to a nasogastric tube (≥16-French).
6. Give the mixture right away through the nasogastric tube into the stomach. After giving the mixture, flush the nasogastric tube with 20 mL of additional water.
7. Do not save the mixture for later use. Discard the unused portion immediately.

How should I store EZALLOR SPRINKLE?

- Store EZALLOR SPRINKLE at room temperature between 68ºF to 77ºF (20ºC to 25ºC).
- Store in a dry place.

Keep EZALLOR SPRINKLE and all medicines out of the reach of children.

This Instructions for Use has been approved by the U.S. Food and Drug Administration.

Distributed by:

Sun Pharmaceutical Industries, Inc.

Cranbury, NJ 08512

Manufactured by:

Sun Pharmaceutical Industries Limited,.

Halol-Baroda Highway,

Halol-389 350, Gujarat, India.

Version: 02/2025

FDA-04

EZALLOR SPRINKLE is a registered trademark of Sun Pharmaceutical Industries Limited.

PACKAGE LABEL.PRINCIPAL DISPLAY PANEL - Label - 5 mg

NDC 47335-984-83
Ezallor Sprinkle TM
(rosuvastatin) Capsules
5 mg
PHARMACIST: Please dispense with Patient Information provided separately to each patient.
Rx only
30 Capsules
SUN PHARMA

PACKAGE LABEL.PRINCIPAL DISPLAY PANEL - Carton - 5 mg

NDC 47335-984-64

Ezallor SprinkleTM
(rosuvastatin) Capsules

5 mg

PHARMACIST: Please dispense with Patient Information provided separately to each patient.

Rx only

30 (3 × 10) Unit-Dose Capsules

SUN PHARMA

PACKAGE LABEL.PRINCIPAL DISPLAY PANEL - Label - 10 mg

NDC 47335-985-83

Ezallor Sprinkle TM
(rosuvastatin) Capsules

10 mg

PHARMACIST: Please dispense with Patient Information provided separately to each patient.

Rx only

30 Capsules

SUN PHARMA

PACKAGE LABEL.PRINCIPAL DISPLAY PANEL - Carton - 10 mg

NDC 47335-985-64

EzallorSprinkleTM
(rosuvastatin) Capsules

10 mg

PHARMACIST: Please dispense with Patient Information provided separately to each patient.

Rx only

30 (3 × 10) Unit-Dose Capsules

SUN PHARMA

PACKAGE LABEL.PRINCIPAL DISPLAY PANEL - Label - 20 mg

NDC 47335-986-83
Ezallor SprinkleTM
(rosuvastatin) Capsules
20 mg*
PHARMACIST: Please dispense with Patient Information provided separately to each patient.
Rx only
30 Capsules
SUN PHARMA

PACKAGE LABEL.PRINCIPAL DISPLAY PANEL - Carton - 20 mg

NDC 47335-986-64
EzallorSprinkleTM
(rosuvastatin) Capsules
20 mg
PHARMACIST: Please dispense with Patient Information provided separately to each patient.
Rx only
30 (3 × 10) Unit-Dose Capsules
SUN PHARMA

PACKAGE LABEL.PRINCIPAL DISPLAY PANEL - Label - 40 mg

NDC 47335-987-83
Ezallor SprinkleTM
(rosuvastatin) Capsules
40 mg*
PHARMACIST: Please dispense with Patient Information provided separately to each patient.
Rx only
30 Capsules
SUN PHARMA

PACKAGE LABEL.PRINCIPAL DISPLAY PANEL - Carton - 40 mg

NDC 47335-987-64
Ezallor SprinkleTM
(rosuvastatin) Capsules
40 mg
PHARMACIST: Please dispense with Patient Information provided separately to each patient.
Rx only
30 (3 × 10) Unit-Dose Capsules
SUN PHARMA